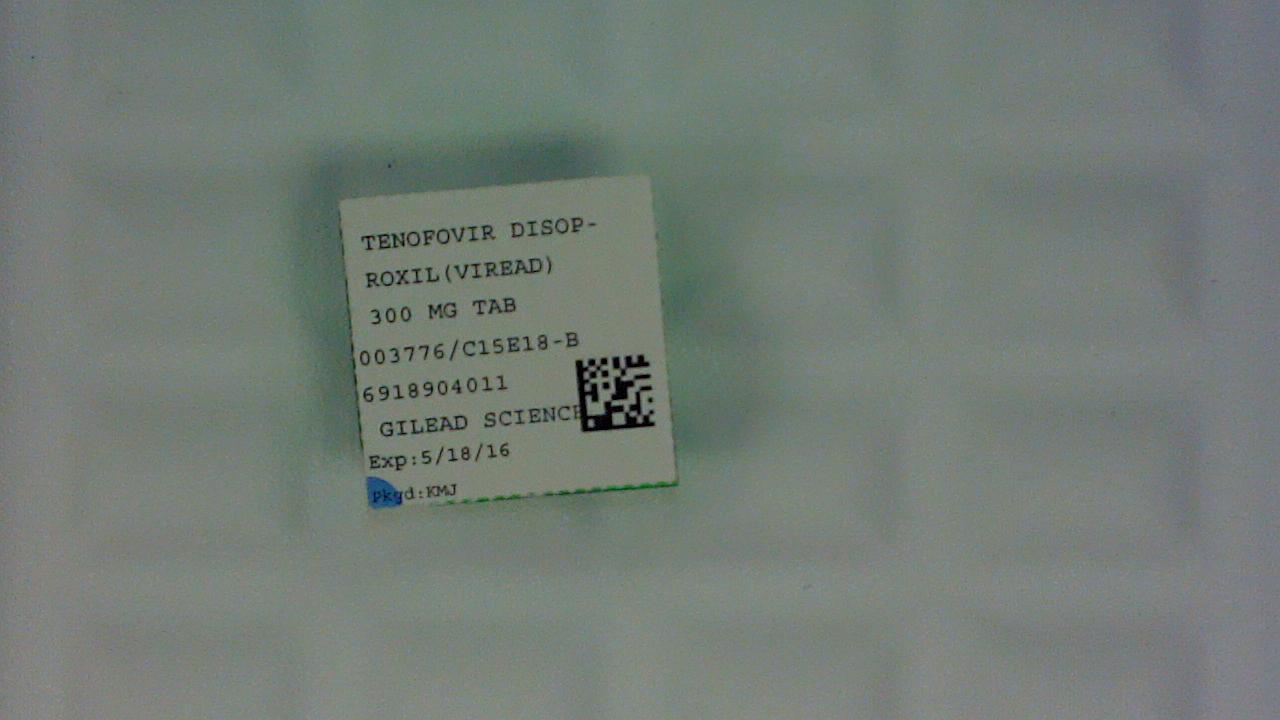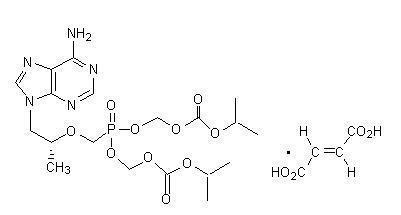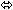 DRUG LABEL: Viread
NDC: 69189-0401 | Form: TABLET, COATED
Manufacturer: Avera McKennan Hospital
Category: prescription | Type: HUMAN PRESCRIPTION DRUG LABEL
Date: 20151124

ACTIVE INGREDIENTS: TENOFOVIR DISOPROXIL FUMARATE 300 mg/1 1
INACTIVE INGREDIENTS: STARCH, CORN; CROSCARMELLOSE SODIUM; LACTOSE MONOHYDRATE; CELLULOSE, MICROCRYSTALLINE; MAGNESIUM STEARATE; FD&C BLUE NO. 2; ALUMINUM OXIDE; TITANIUM DIOXIDE; TRIACETIN; HYPROMELLOSE 2910 (15000 MPA.S)

HIGHLIGHTS OF PRESCRIBING INFORMATION

These highlights do not include all the information needed to use VIREAD safely and effectively. See full prescribing information for VIREAD.
VIREAD® (tenofovir disoproxil fumarate) tablets, for oral use
VIREAD® (tenofovir disoproxil fumarate) powder, for oral use
Initial U.S. Approval: 2001

WARNING: LACTIC ACIDOSIS/SEVERE HEPATOMEGALY WITH STEATOSIS and POST TREATMENT EXACERBATION OF HEPATITIS

See full prescribing information for complete boxed warning.

- Lactic acidosis and severe hepatomegaly with steatosis, including fatal cases, have been reported with the use of nucleoside analogs, including VIREAD. (5.1)
- Severe acute exacerbations of hepatitis have been reported in HBV-infected patients who have discontinued anti-hepatitis B therapy, including VIREAD. Hepatic function should be monitored closely in these patients. If appropriate, resumption of anti-hepatitis B therapy may be warranted. (5.2)

1 INDICATIONS AND USAGE

VIREAD is a nucleotide analog HIV-1 reverse transcriptase inhibitor and an HBV reverse transcriptase inhibitor.

VIREAD is indicated in combination with other antiretroviral agents for the treatment of HIV-1 infection in adults and pediatric patients 2 years of age and older. (1)

VIREAD is indicated for the treatment of chronic hepatitis B in adults and pediatric patients 12 years of age and older. (1)

2 DOSAGE AND ADMINISTRATION

- Recommended dose for the treatment of HIV-1 or chronic hepatitis B in adults and pediatric patients 12 years of age and older (35 kg or more): 300 mg once daily taken orally without regard to food. (2.1)
- Recommended dose for the treatment of HIV-1 in pediatric patients (2 to less than 12 years of age):
  Tablets: for pediatric patients weighing greater than or equal to 17 kg who can swallow an intact tablet, one VIREAD tablet (150, 200, 250 or 300 mg based on body weight) once daily taken orally without regard to food. (2.2)
  Oral powder: 8 mg/kg VIREAD oral powder (up to a maximum of 300 mg) once daily with food. (2.2)
- Dose recommended in renal impairment in adults:
  Creatinine clearance 30–49 mL/min: 300 mg every 48 hours. (2.3)
  Creatinine clearance 10–29 mL/min: 300 mg every 72 to 96 hours. (2.3)
  Hemodialysis: 300 mg every 7 days or after approximately 12 hours of dialysis. (2.3)

3 DOSAGE FORMS AND STRENGTHS

Tablets: 150, 200, 250 and 300 mg (3)

Oral Powder: 40 mg per 1 g of oral powder (3)

4 CONTRAINDICATIONS

None. (4)

5 WARNINGS AND PRECAUTIONS

- New onset or worsening renal impairment: Can include acute renal failure and Fanconi syndrome. Assess estimated creatinine clearance before initiating treatment with VIREAD. In patients at risk for renal dysfunction, assess estimated creatinine clearance, serum phosphorus, urine glucose and urine protein before initiating treatment with VIREAD and periodically during treatment. Avoid administering VIREAD with concurrent or recent use of nephrotoxic drugs. (5.3)
- Coadministration with Other Products: Do not use with other tenofovir-containing products (e.g., ATRIPLA, COMPLERA, STRIBILD and TRUVADA). Do not administer in combination with HEPSERA. (5.4)
- HIV testing: HIV antibody testing should be offered to all HBV-infected patients before initiating therapy with VIREAD. VIREAD should only be used as part of an appropriate antiretroviral combination regimen in HIV-infected patients with or without HBV coinfection. (5.5)
- Decreases in bone mineral density (BMD): Consider assessment of BMD in patients with a history of pathologic fracture or other risk factors for osteoporosis or bone loss. (5.6)
- Redistribution/accumulation of body fat: Observed in HIV-infected patients receiving antiretroviral combination therapy. (5.7)
- Immune reconstitution syndrome: Observed in HIV-infected patients. May necessitate further evaluation and treatment. (5.8)
- Triple nucleoside-only regimens: Early virologic failure has been reported in HIV-infected patients. Monitor carefully and consider treatment modification. (5.9)

6 ADVERSE REACTIONS

In HIV-infected adult subjects: Most common adverse reactions (incidence greater than or equal to 10%, Grades 2–4) are rash, diarrhea, headache, pain, depression, asthenia, and nausea. (6.1)

In HBV-infected subjects with compensated liver disease: most common adverse reaction (all grades) was nausea (9%). (6.1)

In pediatric subjects: Adverse reactions in pediatric subjects were consistent with those observed in adults. (6.1)

In HBV-infected subjects with decompensated liver disease: most common adverse reactions (incidence greater than or equal to 10%, all grades) were abdominal pain, nausea, insomnia, pruritus, vomiting, dizziness, and pyrexia. (6.1)

To report SUSPECTED ADVERSE REACTIONS, contact Gilead Sciences, Inc. at 1-800-GILEAD-5 or FDA at 1-800-FDA-1088 or www.fda.gov/medwatch

7 DRUG INTERACTIONS

- Didanosine: Coadministration increases didanosine concentrations. Use with caution and monitor for evidence of didanosine toxicity (e.g., pancreatitis, neuropathy). Consider dose reductions or discontinuations of didanosine if warranted. (7.1)
- HIV-1 protease inhibitors: Coadministration decreases atazanavir concentrations and increases tenofovir concentrations. When coadministered with VIREAD, use atazanavir given with ritonavir. Coadministration of VIREAD with atazanavir and ritonavir, darunavir and ritonavir, or lopinavir/ritonavir increases tenofovir concentrations. Monitor for evidence of tenofovir toxicity. (7.2)

8 USE IN SPECIFIC POPULATIONS

- Nursing mothers: Women infected with HIV should be instructed not to breast feed. (8.3)

FULL PRESCRIBING INFORMATION

WARNING: LACTIC ACIDOSIS/SEVERE HEPATOMEGALY WITH STEATOSIS and POST TREATMENT EXACERBATION OF HEPATITIS

Lactic acidosis and severe hepatomegaly with steatosis, including fatal cases, have been reported with the use of nucleoside analogs, including VIREAD, in combination with other antiretrovirals [See Warnings and Precautions (5.1)].

Severe acute exacerbations of hepatitis have been reported in HBV-infected patients who have discontinued anti-hepatitis B therapy, including VIREAD. Hepatic function should be monitored closely with both clinical and laboratory follow-up for at least several months in patients who discontinue anti-hepatitis B therapy, including VIREAD. If appropriate, resumption of anti-hepatitis B therapy may be warranted [See Warnings and Precautions (5.2)].

1 INDICATIONS AND USAGE

1.1 HIV-1 Infection

VIREAD is indicated in combination with other antiretroviral agents for the treatment of HIV-1 infection in adults and pediatric patients 2 years of age and older.

The following points should be considered when initiating therapy with VIREAD for the treatment of HIV-1 infection:

- VIREAD should not be used in combination with ATRIPLA®, COMPLERA®, STRIBILD®, or TRUVADA® [See Warnings and Precautions (5.4)].

1.2 Chronic Hepatitis B

VIREAD is indicated for the treatment of chronic hepatitis B in adults and pediatric patients 12 years of age and older.

The following points should be considered when initiating therapy with VIREAD for the treatment of HBV infection:

- The indication in adults is based on safety and efficacy data from treatment of subjects who were nucleoside-treatment-naïve and subjects who were treatment-experienced with documented resistance to lamivudine. Subjects were adults with HBeAg-positive and HBeAg-negative chronic hepatitis B with compensated liver disease [See Clinical Studies (14.2)].
- VIREAD was evaluated in a limited number of subjects with chronic hepatitis B and decompensated liver disease [See Adverse Reactions (6.1), Clinical Studies (14.2)].
- The numbers of subjects in clinical trials who had adefovir resistance-associated substitutions at baseline were too small to reach conclusions of efficacy [See Microbiology (12.4), Clinical Studies (14.2)].

2 DOSAGE AND ADMINISTRATION

2.1 Recommended Dose in Adults and Pediatric Patients 12 Years of Age and Older (35 kg or more)

For the treatment of HIV-1 or chronic hepatitis B: The dose is one 300 mg VIREAD tablet once daily taken orally, without regard to food.

For patients unable to swallow VIREAD tablets, the oral powder formulation (7.5 scoops) may be used.

In the treatment of chronic hepatitis B, the optimal duration of treatment is unknown. Safety and efficacy in pediatric patients with chronic hepatitis B weighing less than 35 kg have not been established.

2.2 Recommended Dose in Pediatric Patients 2 Years to Less than 12 Years of Age

HIV-1 Infection

For the treatment of HIV-1 in pediatric patients 2 years of age and older, the recommended oral dose of VIREAD is 8 mg of tenofovir disoproxil fumarate per kilogram of body weight (up to a maximum of 300 mg) once daily administered as oral powder or tablets.

VIREAD oral powder should be measured only with the supplied dosing scoop. One level scoop delivers 1 g of powder which contains 40 mg of tenofovir disoproxil fumarate. VIREAD oral powder should be mixed in a container with 2 to 4 ounces of soft food not requiring chewing (e.g., applesauce, baby food, yogurt). The entire mixture should be ingested immediately to avoid a bitter taste. Do not administer VIREAD oral powder in a liquid as the powder may float on top of the liquid even after stirring. Further patient instructions on how to administer VIREAD oral powder with the supplied dosing scoop are provided in the FDA-approved patient labeling (Patient Information).

VIREAD is also available as tablets in 150, 200, 250 and 300 mg strengths for pediatric patients who weigh greater than or equal to 17 kg and who are able to reliably swallow intact tablets. The dose is one tablet once daily taken orally, without regard to food.

Tables 1 and 2 contain dosing recommendations for VIREAD oral powder and tablets based on body weight. Weight should be monitored periodically and the VIREAD dose adjusted accordingly.

Table 1 Dosing Recommendations for Pediatric Patients ≥2 Years of Age Using VIREAD Oral Powder
Body Weight Kilogram (kg) | Oral Powder Once Daily Scoops of Powder
10 to <12 | 2
12 to <14 | 2.5
14 to <17 | 3
17 to <19 | 3.5
19 to <22 | 4
22 to <24 | 4.5
24 to <27 | 5
27 to <29 | 5.5
29 to <32 | 6
32 to <34 | 6.5
34 to <35 | 7
≥35 | 7.5

Table 2 Dosing Recommendations for Pediatric Patients ≥2 Years of Age and Weighing ≥17 kg Using VIREAD Tablets
Body Weight Kilogram (kg) | Tablets Once Daily
17 to <22 | 150 mg
22 to <28 | 200 mg
28 to <35 | 250 mg
≥35 | 300 mg

Chronic Hepatitis B

Safety and efficacy of VIREAD in patients younger than 12 years of age have not been established.

2.3 Dose Adjustment for Renal Impairment in Adults

Significantly increased drug exposures occurred when VIREAD was administered to subjects with moderate to severe renal impairment [See Clinical Pharmacology (12.3)]. Therefore, the dosing interval of VIREAD tablets 300 mg should be adjusted in patients with baseline creatinine clearance below 50 mL/min using the recommendations in Table 3. These dosing interval recommendations are based on modeling of single-dose pharmacokinetic data in non-HIV and non-HBV infected subjects with varying degrees of renal impairment, including end-stage renal disease requiring hemodialysis. The safety and effectiveness of these dosing interval adjustment recommendations have not been clinically evaluated in patients with moderate or severe renal impairment, therefore clinical response to treatment and renal function should be closely monitored in these patients [See Warnings and Precautions (5.3)]. There are no data to recommend use of VIREAD tablets 150, 200 or 250 mg or VIREAD oral powder in patients with renal impairment.

No dose adjustment of VIREAD tablets 300 mg is necessary for patients with mild renal impairment (creatinine clearance 50–80 mL/min). Routine monitoring of estimated creatinine clearance, serum phosphorus, urine glucose, and urine protein should be performed in patients with mild renal impairment [See Warnings and Precautions (5.3)].

Table 3 Dosage Adjustment for Patients with Altered Creatinine Clearance
 | Creatinine Clearance (mL/min) [Calculated using ideal (lean) body weight.]
 | ≥50 | 30–49 | 10–29 | Hemodialysis Patients
Recommended 300 mg Dosing Interval | Every 24 hours | Every 48 hours | Every 72 to 96 hours | Every 7 days or after a total of approximately 12 hours of dialysis [Generally once weekly assuming three hemodialysis sessions a week of approximately 4 hours duration. VIREAD should be administered following completion of dialysis.]

The pharmacokinetics of tenofovir have not been evaluated in non-hemodialysis patients with creatinine clearance below 10 mL/min; therefore, no dosing recommendation is available for these patients.

No data are available to make dose recommendations in pediatric patients with renal impairment.

3 DOSAGE FORMS AND STRENGTHS

VIREAD is available as tablets or as an oral powder.

VIREAD tablets 150 mg contain 150 mg of tenofovir disoproxil fumarate, which is equivalent to 123 mg of tenofovir disoproxil. The tablets are triangle-shaped, white, film-coated, and debossed with "GSI" on one side and "150" on the other side.

VIREAD tablets 200 mg contain 200 mg of tenofovir disoproxil fumarate, which is equivalent to 163 mg of tenofovir disoproxil. The tablets are round-shaped, white, film-coated, and debossed with "GSI" on one side and "200" on the other side.

VIREAD tablets 250 mg contain 250 mg of tenofovir disoproxil fumarate, which is equivalent to 204 mg of tenofovir disoproxil. The tablets are capsule-shaped, white, film-coated, and debossed with "GSI" on one side and "250" on the other side.

VIREAD tablets 300 mg contain 300 mg of tenofovir disoproxil fumarate, which is equivalent to 245 mg of tenofovir disoproxil. The tablets are almond-shaped, light blue, film-coated, and debossed with "GILEAD" and "4331" on one side and with "300" on the other side.

The oral powder consists of white, taste-masked, coated granules containing 40 mg of tenofovir disoproxil fumarate, which is equivalent to 33 mg of tenofovir disoproxil, per level scoop. Each level scoop contains 1 gram of oral powder.

4 CONTRAINDICATIONS

None.

5 WARNINGS AND PRECAUTIONS

5.1 Lactic Acidosis/Severe Hepatomegaly with Steatosis

Lactic acidosis and severe hepatomegaly with steatosis, including fatal cases, have been reported with the use of nucleoside analogs, including VIREAD, in combination with other antiretrovirals. A majority of these cases have been in women. Obesity and prolonged nucleoside exposure may be risk factors. Particular caution should be exercised when administering nucleoside analogs to any patient with known risk factors for liver disease; however, cases have also been reported in patients with no known risk factors. Treatment with VIREAD should be suspended in any patient who develops clinical or laboratory findings suggestive of lactic acidosis or pronounced hepatotoxicity (which may include hepatomegaly and steatosis even in the absence of marked transaminase elevations).

5.2 Exacerbation of Hepatitis after Discontinuation of Treatment

Discontinuation of anti-HBV therapy, including VIREAD, may be associated with severe acute exacerbations of hepatitis. Patients infected with HBV who discontinue VIREAD should be closely monitored with both clinical and laboratory follow-up for at least several months after stopping treatment. If appropriate, resumption of anti-hepatitis B therapy may be warranted.

5.3 New Onset or Worsening Renal Impairment

Tenofovir is principally eliminated by the kidney. Renal impairment, including cases of acute renal failure and Fanconi syndrome (renal tubular injury with severe hypophosphatemia), has been reported with the use of VIREAD [See Adverse Reactions (6.2)].

It is recommended that estimated creatinine clearance be assessed in all patients prior to initiating therapy and as clinically appropriate during therapy with VIREAD. In patients at risk of renal dysfunction, including patients who have previously experienced renal events while receiving HEPSERA®, it is recommended that estimated creatinine clearance, serum phosphorus, urine glucose, and urine protein be assessed prior to initiation of VIREAD, and periodically during VIREAD therapy.

Dosing interval adjustment of VIREAD and close monitoring of renal function are recommended in all patients with creatinine clearance below 50 mL/min [See Dosage and Administration (2.3)]. No safety or efficacy data are available in patients with renal impairment who received VIREAD using these dosing guidelines, so the potential benefit of VIREAD therapy should be assessed against the potential risk of renal toxicity.

VIREAD should be avoided with concurrent or recent use of a nephrotoxic agent (e.g., high-dose or multiple non-steroidal anti-inflammatory drugs (NSAIDs)) [See Drug Interactions (7.3)]. Cases of acute renal failure after initiation of high dose or multiple NSAIDs have been reported in HIV-infected patients with risk factors for renal dysfunction who appeared stable on tenofovir DF. Some patients required hospitalization and renal replacement therapy. Alternatives to NSAIDs should be considered, if needed, in patients at risk for renal dysfunction.

Persistent or worsening bone pain, pain in extremities, fractures and/or muscular pain or weakness may be manifestations of proximal renal tubulopathy and should prompt an evaluation of renal function in at-risk patients.

5.4 Coadministration with Other Products

VIREAD should not be used in combination with the fixed-dose combination products ATRIPLA, COMPLERA, STRIBILD, or TRUVADA since tenofovir disoproxil fumarate is a component of these products.

VIREAD should not be administered in combination with HEPSERA (adefovir dipivoxil) [See Drug Interactions (7.3)].

5.5 Patients Coinfected with HIV-1 and HBV

Due to the risk of development of HIV-1 resistance, VIREAD should only be used in HIV-1 and HBV coinfected patients as part of an appropriate antiretroviral combination regimen.

HIV-1 antibody testing should be offered to all HBV-infected patients before initiating therapy with VIREAD. It is also recommended that all patients with HIV-1 be tested for the presence of chronic hepatitis B before initiating treatment with VIREAD.

5.6 Bone Effects

Bone Mineral Density:

In clinical trials in HIV-1 infected adults, VIREAD was associated with slightly greater decreases in bone mineral density (BMD) and increases in biochemical markers of bone metabolism, suggesting increased bone turnover relative to comparators. Serum parathyroid hormone levels and 1,25 Vitamin D levels were also higher in subjects receiving VIREAD [See Adverse Reactions (6.1)].

Clinical trials evaluating VIREAD in pediatric and adolescent subjects were conducted. Under normal circumstances, BMD increases rapidly in pediatric patients. In HIV-1 infected subjects aged 2 years to less than 18 years, bone effects were similar to those observed in adult subjects and suggest increased bone turnover. Total body BMD gain was less in the VIREAD-treated HIV-1 infected pediatric subjects as compared to the control groups. Similar trends were observed in chronic hepatitis B infected adolescent subjects aged 12 years to less than 18 years. In all pediatric trials, skeletal growth (height) appeared to be unaffected [See Adverse Reactions (6.1)].

The effects of VIREAD-associated changes in BMD and biochemical markers on long-term bone health and future fracture risk are unknown. Assessment of BMD should be considered for adults and pediatric patients who have a history of pathologic bone fracture or other risk factors for osteoporosis or bone loss. Although the effect of supplementation with calcium and vitamin D was not studied, such supplementation may be beneficial for all patients. If bone abnormalities are suspected then appropriate consultation should be obtained.

Mineralization Defects:

Cases of osteomalacia associated with proximal renal tubulopathy, manifested as bone pain or pain in extremities and which may contribute to fractures, have been reported in association with the use of VIREAD [See Adverse Reactions (6.2)]. Arthralgias and muscle pain or weakness have also been reported in cases of proximal renal tubulopathy. Hypophosphatemia and osteomalacia secondary to proximal renal tubulopathy should be considered in patients at risk of renal dysfunction who present with persistent or worsening bone or muscle symptoms while receiving products containing tenofovir DF [See Warnings and Precautions (5.3)].

5.7 Fat Redistribution

In HIV-infected patients redistribution/accumulation of body fat including central obesity, dorsocervical fat enlargement (buffalo hump), peripheral wasting, facial wasting, breast enlargement, and "cushingoid appearance" have been observed in patients receiving combination antiretroviral therapy. The mechanism and long-term consequences of these events are currently unknown. A causal relationship has not been established.

5.8 Immune Reconstitution Syndrome

Immune reconstitution syndrome has been reported in HIV-infected patients treated with combination antiretroviral therapy, including VIREAD. During the initial phase of combination antiretroviral treatment, patients whose immune system responds may develop an inflammatory response to indolent or residual opportunistic infections [such as Mycobacterium avium infection, cytomegalovirus, Pneumocystis jirovecii pneumonia (PCP), or tuberculosis], which may necessitate further evaluation and treatment.

Autoimmune disorders (such as Graves' disease, polymyositis, and Guillain-Barré syndrome) have also been reported to occur in the setting of immune reconstitution, however, the time to onset is more variable, and can occur many months after initiation of treatment.

5.9 Early Virologic Failure

Clinical trials in HIV-infected subjects have demonstrated that certain regimens that only contain three nucleoside reverse transcriptase inhibitors (NRTI) are generally less effective than triple drug regimens containing two NRTIs in combination with either a non-nucleoside reverse transcriptase inhibitor or a HIV-1 protease inhibitor. In particular, early virological failure and high rates of resistance substitutions have been reported. Triple nucleoside regimens should therefore be used with caution. Patients on a therapy utilizing a triple nucleoside-only regimen should be carefully monitored and considered for treatment modification.

6 ADVERSE REACTIONS

The following adverse reactions are discussed in other sections of the labeling:

- Lactic Acidosis/Severe Hepatomegaly with Steatosis [See Boxed Warning, Warnings and Precautions (5.1)].
- Severe Acute Exacerbation of Hepatitis [See Boxed Warning, Warnings and Precautions (5.2)].
- New Onset or Worsening Renal Impairment [See Warnings and Precautions (5.3)].
- Bone Effects [See Warnings and Precautions (5.6)].
- Immune Reconstitution Syndrome [See Warnings and Precautions (5.8)].

6.1 Adverse Reactions from Clinical Trials Experience

Because clinical trials are conducted under widely varying conditions, adverse reaction rates observed in the clinical trials of a drug cannot be directly compared to rates in the clinical trials of another drug and may not reflect the rates observed in practice.

Clinical Trials in Adult Patients with HIV-1 Infection

More than 12,000 subjects have been treated with VIREAD alone or in combination with other antiretroviral medicinal products for periods of 28 days to 215 weeks in clinical trials and expanded access programs. A total of 1,544 subjects have received VIREAD 300 mg once daily in clinical trials; over 11,000 subjects have received VIREAD in expanded access programs.

The most common adverse reactions (incidence greater than or equal to 10%, Grades 2–4) identified from any of the 3 large controlled clinical trials include rash, diarrhea, headache, pain, depression, asthenia, and nausea.

Treatment-Naïve Patients

Study 903 - Treatment-Emergent Adverse Reactions: The most common adverse reactions seen in a double-blind comparative controlled trial in which 600 treatment-naïve subjects received VIREAD (N=299) or stavudine (N=301) in combination with lamivudine and efavirenz for 144 weeks (Study 903) were mild to moderate gastrointestinal events and dizziness.

Mild adverse reactions (Grade 1) were common with a similar incidence in both arms, and included dizziness, diarrhea, and nausea. Selected treatment-emergent moderate to severe adverse reactions are summarized in Table 4.

Table 4 Selected Treatment-Emergent Adverse Reactions [Frequencies of adverse reactions are based on all treatment-emergent adverse events, regardless of relationship to study drug.] (Grades 2–4) Reported in ≥5% in Any Treatment Group in Study 903 (0–144 Weeks)
 | VIREAD + 3TC + EFV | d4T + 3TC + EFV
 | N=299 | N=301
Body as a Whole
Headache | 14% | 17%
Pain | 13% | 12%
Fever | 8% | 7%
Abdominal pain | 7% | 12%
Back pain | 9% | 8%
Asthenia | 6% | 7%
Digestive System
Diarrhea | 11% | 13%
Nausea | 8% | 9%
Dyspepsia | 4% | 5%
Vomiting | 5% | 9%
Metabolic Disorders
Lipodystrophy [Lipodystrophy represents a variety of investigator-described adverse events not a protocol-defined syndrome.] | 1% | 8%
Musculoskeletal
Arthralgia | 5% | 7%
Myalgia | 3% | 5%
Nervous System
Depression | 11% | 10%
Insomnia | 5% | 8%
Dizziness | 3% | 6%
Peripheral neuropathy [Peripheral neuropathy includes peripheral neuritis and neuropathy.] | 1% | 5%
Anxiety | 6% | 6%
Respiratory
Pneumonia | 5% | 5%
Skin and Appendages
Rash event [Rash event includes rash, pruritus, maculopapular rash, urticaria, vesiculobullous rash, and pustular rash.] | 18% | 12%

Laboratory Abnormalities: With the exception of fasting cholesterol and fasting triglyceride elevations that were more common in the stavudine group (40% and 9%) compared with VIREAD (19% and 1%) respectively, laboratory abnormalities observed in this trial occurred with similar frequency in the VIREAD and stavudine treatment arms. A summary of Grades 3–4 laboratory abnormalities is provided in Table 5.

Table 5 Grades 3–4 Laboratory Abnormalities Reported in ≥1% of VIREAD-Treated Subjects in Study 903 (0–-144 Weeks)
 | VIREAD + 3TC + EFV | d4T + 3TC + EFV
 | N=299 | N=301
Any ≥ Grade 3 Laboratory Abnormality | 36% | 42%
Fasting Cholesterol (>240 mg/dL) | 19% | 40%
Creatine Kinase (M: >990 U/L; F: >845 U/L) | 12% | 12%
Serum Amylase (>175 U/L) | 9% | 8%
AST (M: >180 U/L; F: >170 U/L) | 5% | 7%
ALT (M: >215 U/L; F: >170 U/L) | 4% | 5%
Hematuria (>100 RBC/HPF) | 7% | 7%
Neutrophils (<750/mm^3) | 3% | 1%
Fasting Triglycerides (>750 mg/dL) | 1% | 9%

Study 934 – Treatment-Emergent Adverse Reactions: In Study 934, 511 antiretroviral-naïve subjects received either VIREAD + EMTRIVA® administered in combination with efavirenz (N=257) or zidovudine/lamivudine administered in combination with efavirenz (N=254). Adverse reactions observed in this trial were generally consistent with those seen in previous studies in treatment-experienced or treatment-naïve subjects (Table 6).

Changes in Bone Mineral Density:

In HIV-1 infected adult subjects in Study 903, there was a significantly greater mean percentage decrease from baseline in BMD at the lumbar spine in subjects receiving VIREAD + lamivudine + efavirenz (-2.2% ± 3.9) compared with subjects receiving stavudine + lamivudine + efavirenz (-1.0% ± 4.6) through 144 weeks. Changes in BMD at the hip were similar between the two treatment groups (-2.8% ± 3.5 in the VIREAD group vs. -2.4% ± 4.5 in the stavudine group). In both groups, the majority of the reduction in BMD occurred in the first 24–48 weeks of the trial and this reduction was sustained through Week 144. Twenty-eight percent of VIREAD-treated subjects vs. 21% of the stavudine-treated subjects lost at least 5% of BMD at the spine or 7% of BMD at the hip. Clinically relevant fractures (excluding fingers and toes) were reported in 4 subjects in the VIREAD group and 6 subjects in the stavudine group. In addition, there were significant increases in biochemical markers of bone metabolism (serum bone-specific alkaline phosphatase, serum osteocalcin, serum C telopeptide, and urinary N telopeptide) and higher serum parathyroid hormone levels and 1,25 Vitamin D levels in the VIREAD group relative to the stavudine group; however, except for bone-specific alkaline phosphatase, these changes resulted in values that remained within the normal range [See Warnings and Precautions (5.6)].

Table 6 Selected Treatment-Emergent Adverse Reactions [Frequencies of adverse reactions are based on all treatment-emergent adverse events, regardless of relationship to study drug.] (Grades 2–4) Reported in ≥5% in Any Treatment Group in Study 934 (0–144 Weeks)
 | VIREAD [From Weeks 96 to 144 of the trial, subjects received TRUVADA with efavirenz in place of VIREAD + EMTRIVA with efavirenz.] + FTC + EFV | AZT/3TC + EFV
 | N=257 | N=254
Gastrointestinal Disorder
Diarrhea | 9% | 5%
Nausea | 9% | 7%
Vomiting | 2% | 5%
General Disorders and Administration Site Condition
Fatigue | 9% | 8%
Infections and Infestations
Sinusitis | 8% | 4%
Upper respiratory tract infections | 8% | 5%
Nasopharyngitis | 5% | 3%
Nervous System Disorders
Headache | 6% | 5%
Dizziness | 8% | 7%
Psychiatric Disorders
Depression | 9% | 7%
Insomnia | 5% | 7%
Skin and Subcutaneous Tissue Disorders
Rash event [Rash event includes rash, exfoliative rash, rash generalized, rash macular, rash maculopapular, rash pruritic, and rash vesicular.] | 7% | 9%

Laboratory Abnormalities: Laboratory abnormalities observed in this trial were generally consistent with those seen in previous trials (Table 7).

Table 7 Significant Laboratory Abnormalities Reported in ≥1% of Subjects in Any Treatment Group in Study 934 (0–144 Weeks)
 | VIREAD [From Weeks 96 to 144 of the trial, subjects received TRUVADA with efavirenz in place of VIREAD + EMTRIVA with efavirenz.] + FTC + EFV | AZT/3TC + EFV
 | N=257 | N=254
Any ≥ Grade 3 Laboratory Abnormality | 30% | 26%
Fasting Cholesterol (>240 mg/dL) | 22% | 24%
Creatine Kinase (M: >990 U/L; F: >845 U/L) | 9% | 7%
Serum Amylase (>175 U/L) | 8% | 4%
Alkaline Phosphatase (>550 U/L) | 1% | 0%
AST (M: >180 U/L; F: >170 U/L) | 3% | 3%
ALT (M: >215 U/L; F: >170 U/L) | 2% | 3%
Hemoglobin (<8.0 mg/dL) | 0% | 4%
Hyperglycemia (>250 mg/dL) | 2% | 1%
Hematuria (>75 RBC/HPF) | 3% | 2%
Glycosuria (≥3+) | <1% | 1%
Neutrophils (<750/mm^3) | 3% | 5%
Fasting Triglycerides (>750 mg/dL) | 4% | 2%

Treatment-Experienced Patients

Treatment-Emergent Adverse Reactions: The adverse reactions seen in treatment-experienced subjects were generally consistent with those seen in treatment-naïve subjects including mild to moderate gastrointestinal events, such as nausea, diarrhea, vomiting, and flatulence. Less than 1% of subjects discontinued participation in the clinical trials due to gastrointestinal adverse reactions (Study 907).

A summary of moderate to severe, treatment-emergent adverse reactions that occurred during the first 48 weeks of Study 907 is provided in Table 8.

Table 8 Selected Treatment-Emergent Adverse Reactions [Frequencies of adverse reactions are based on all treatment-emergent adverse events, regardless of relationship to study drug.] (Grades 2–4) Reported in ≥3% in Any Treatment Group in Study 907 (0–48 Weeks)
 | VIREAD (N=368) (Week 0–24) | Placebo (N=182) (Week 0–24) | VIREAD (N=368) (Week 0–48) | Placebo Crossover to VIREAD (N=170) (Week 24–48)
Body as a Whole
Asthenia | 7% | 6% | 11% | 1%
Pain | 7% | 7% | 12% | 4%
Headache | 5% | 5% | 8% | 2%
Abdominal pain | 4% | 3% | 7% | 6%
Back pain | 3% | 3% | 4% | 2%
Chest pain | 3% | 1% | 3% | 2%
Fever | 2% | 2% | 4% | 2%
Digestive System
Diarrhea | 11% | 10% | 16% | 11%
Nausea | 8% | 5% | 11% | 7%
Vomiting | 4% | 1% | 7% | 5%
Anorexia | 3% | 2% | 4% | 1%
Dyspepsia | 3% | 2% | 4% | 2%
Flatulence | 3% | 1% | 4% | 1%
Respiratory
Pneumonia | 2% | 0% | 3% | 2%
Nervous System
Depression | 4% | 3% | 8% | 4%
Insomnia | 3% | 2% | 4% | 4%
Peripheral neuropathy [Peripheral neuropathy includes peripheral neuritis and neuropathy.] | 3% | 3% | 5% | 2%
Dizziness | 1% | 3% | 3% | 1%
Skin and Appendage
Rash event [Rash event includes rash, pruritus, maculopapular rash, urticaria, vesiculobullous rash, and pustular rash.] | 5% | 4% | 7% | 1%
Sweating | 3% | 2% | 3% | 1%
Musculoskeletal
Myalgia | 3% | 3% | 4% | 1%
Metabolic
Weight loss | 2% | 1% | 4% | 2%

Laboratory Abnormalities: Laboratory abnormalities observed in this trial occurred with similar frequency in the VIREAD and placebo-treated groups. A summary of Grades 3–4 laboratory abnormalities is provided in Table 9.

Table 9 Grades 3–4 Laboratory Abnormalities Reported in ≥1% of VIREAD-Treated Subjects in Study 907 (0–48 Weeks)
 | VIREAD (N=368) (Week 0–24) | Placebo (N=182) (Week 0–24) | VIREAD (N=368) (Week 0–48) | Placebo Crossover to VIREAD (N=170) (Week 24–48)
Any ≥ Grade 3 Laboratory Abnormality | 25% | 38% | 35% | 34%
Triglycerides (>750 mg/dL) | 8% | 13% | 11% | 9%
Creatine Kinase (M: >990 U/L; F: >845 U/L) | 7% | 14% | 12% | 12%
Serum Amylase (>175 U/L) | 6% | 7% | 7% | 6%
Glycosuria (≥3+) | 3% | 3% | 3% | 2%
AST (M: >180 U/L; F: >170 U/L) | 3% | 3% | 4% | 5%
ALT (M: >215 U/L; F: >170 U/L) | 2% | 2% | 4% | 5%
Serum Glucose (>250 U/L) | 2% | 4% | 3% | 3%
Neutrophils (<750/mm^3) | 1% | 1% | 2% | 1%

Clinical Trials in Pediatric Subjects 2 Years of Age and Older with HIV-1 Infection

Assessment of adverse reactions is based on two randomized trials (Studies 352 and 321) in 184 HIV-1 infected pediatric subjects (2 to less than 18 years of age) who received treatment with VIREAD (N=93) or placebo/active comparator (N=91) in combination with other antiretroviral agents for 48 weeks. The adverse reactions observed in subjects who received treatment with VIREAD were consistent with those observed in clinical trials in adults.

Eighty-nine pediatric subjects (2 to less than 12 years of age) received VIREAD in Study 352 for a median exposure of 104 weeks. Of these, 4 subjects discontinued from the trial due to adverse reactions consistent with proximal renal tubulopathy. Three of these 4 subjects presented with hypophosphatemia and also had decreases in total body or spine BMD Z score [See Warnings and Precautions (5.6)].

Changes in Bone Mineral Density:

Clinical trials in HIV-1 infected children and adolescents evaluated BMD changes. In Study 321 (12 to less than 18 years), the mean rate of BMD gain at Week 48 was less in the VIREAD compared to the placebo treatment group. Six VIREAD treated subjects and one placebo treated subject had significant (greater than 4%) lumbar spine BMD loss at Week 48. Changes from baseline BMD Z-scores were –0.341 for lumbar spine and –0.458 for total body in the 28 subjects who were treated with VIREAD for 96 weeks. In Study 352 (2 to less than 12 years), the mean rate of BMD gain in lumbar spine at Week 48 was similar between the VIREAD and the d4T or AZT treatment groups. Total body BMD gain was less in the VIREAD compared to the d4T or AZT treatment groups. One VIREAD-treated subject and none of the d4T or AZT-treated subjects experienced significant (greater than 4%) lumbar spine BMD loss at Week 48. Changes from baseline in BMD Z scores were –0.012 for lumbar spine and –0.338 for total body in the 64 subjects who were treated with VIREAD for 96 weeks. In both trials, skeletal growth (height) appeared to be unaffected [See Warnings and Precautions (5.6)].

Clinical Trials in Adult Subjects with Chronic Hepatitis B and Compensated Liver Disease

Treatment-Emergent Adverse Reactions: In controlled clinical trials in 641 subjects with chronic hepatitis B (0102 and 0103), more subjects treated with VIREAD during the 48-week double-blind period experienced nausea: 9% with VIREAD versus 2% with HEPSERA. Other treatment-emergent adverse reactions reported in more than 5% of subjects treated with VIREAD included: abdominal pain, diarrhea, headache, dizziness, fatigue, nasopharyngitis, back pain and skin rash.

During the open-label phase of treatment with VIREAD (weeks 48–384) in Studies 0102 and 0103, 2% of subjects (13/585) experienced a confirmed increase in serum creatinine of 0.5 mg/dL from baseline. No significant change in the tolerability profile was observed with continued treatment for up to 384 weeks.

Laboratory Abnormalities: A summary of Grades 3–4 laboratory abnormalities through Week 48 is provided in Table 10. Grades 3–4 laboratory abnormalities were similar in subjects continuing VIREAD treatment for up to 384 weeks in these trials.

Table 10 Grades 3–4 Laboratory Abnormalities Reported in ≥1% of VIREAD-Treated Subjects in Studies 0102 and 0103 (0–48 Weeks)
 | VIREAD (N=426) | HEPSERA (N=215)
Any ≥ Grade 3 Laboratory Abnormality | 19% | 13%
Creatine Kinase (M: >990 U/L; F: >845 U/L) | 2% | 3%
Serum Amylase (>175 U/L) | 4% | 1%
Glycosuria (≥3+) | 3% | <1%
AST (M: >180 U/L; F: >170 U/L) | 4% | 4%
ALT (M: >215 U/L; F: >170 U/L) | 10% | 6%

The overall incidence of on-treatment ALT flares (defined as serum ALT greater than 2 × baseline and greater than 10 × ULN, with or without associated symptoms) was similar between VIREAD (2.6%) and HEPSERA (2%). ALT flares generally occurred within the first 4–8 weeks of treatment and were accompanied by decreases in HBV DNA levels. No subject had evidence of decompensation. ALT flares typically resolved within 4 to 8 weeks without changes in study medication.

The adverse reactions observed in subjects with chronic hepatitis B and lamivudine resistance who received treatment with VIREAD were consistent with those observed in other hepatitis B clinical trials in adults.

Clinical Trials in Adult Subjects with Chronic Hepatitis B and Decompensated Liver Disease

In a small randomized, double-blind, active-controlled trial (0108), subjects with CHB and decompensated liver disease received treatment with VIREAD or other antiviral drugs for up to 48 weeks [See Clinical Studies (14.2)]. Among the 45 subjects receiving VIREAD, the most frequently reported treatment-emergent adverse reactions of any severity were abdominal pain (22%), nausea (20%), insomnia (18%), pruritus (16%), vomiting (13%), dizziness (13%), and pyrexia (11%). Two of 45 (4%) subjects died through Week 48 of the trial due to progression of liver disease. Three of 45 (7%) subjects discontinued treatment due to an adverse event. Four of 45 (9%) subjects experienced a confirmed increase in serum creatinine of 0.5 mg/dL (1 subject also had a confirmed serum phosphorus less than 2 mg/dL through Week 48). Three of these subjects (each of whom had a Child-Pugh score greater than or equal to 10 and MELD score greater than or equal to 14 at entry) developed renal failure. Because both VIREAD and decompensated liver disease may have an impact on renal function, the contribution of VIREAD to renal impairment in this population is difficult to ascertain.

One of 45 subjects experienced an on-treatment hepatic flare during the 48 Week trial.

Clinical Trials in Pediatric Subjects 12 Years of Age and Older with Chronic Hepatitis B

Assessment of adverse reactions is based on one randomized study (Study GS-US-174-0115) in 106 pediatric subjects (12 to less than 18 years of age) infected with chronic hepatitis B receiving treatment with VIREAD (N = 52) or placebo (N = 54) for 72 weeks. The adverse reactions observed in pediatric subjects who received treatment with VIREAD were consistent with those observed in clinical trials of VIREAD in adults.

In this study, both the VIREAD and placebo treatment arms experienced an overall increase in mean lumbar spine BMD over 72 weeks, as expected for an adolescent population. The BMD gains from baseline to Week 72 in lumbar spine and total body BMD in VIREAD-treated subjects (+5% and +3%, respectively) were less than the BMD gains observed in placebo-treated subjects (+8% and +5%, respectively). Three subjects in the VIREAD group and two subjects in the placebo group had significant (greater than 4%) lumbar spine BMD loss at Week 72. At baseline, mean BMD Z-scores in subjects randomized to VIREAD were −0.43 for lumbar spine and −0.20 for total body, and mean BMD Z-scores in subjects randomized to placebo were −0.28 for lumbar spine and −0.26 for total body. In subjects receiving VIREAD for 72 weeks, the mean change in BMD Z-score was −0.05 for lumbar spine and −0.15 for total body compared to +0.07 and +0.06, respectively, in subjects receiving placebo. As observed in pediatric studies of HIV-infected patients, skeletal growth (height) appeared to be unaffected [See Warnings and Precautions (5.6)].

6.2 Postmarketing Experience

The following adverse reactions have been identified during postapproval use of VIREAD. Because postmarketing reactions are reported voluntarily from a population of uncertain size, it is not always possible to reliably estimate their frequency or establish a causal relationship to drug exposure.

Immune System Disorders
allergic reaction, including angioedema

Metabolism and Nutrition Disorders
lactic acidosis, hypokalemia, hypophosphatemia

Respiratory, Thoracic, and Mediastinal Disorders
dyspnea

Gastrointestinal Disorders
pancreatitis, increased amylase, abdominal pain

Hepatobiliary Disorders
hepatic steatosis, hepatitis, increased liver enzymes (most commonly AST, ALT gamma GT)

Skin and Subcutaneous Tissue Disorders
rash

Musculoskeletal and Connective Tissue Disorders
rhabdomyolysis, osteomalacia (manifested as bone pain and which may contribute to fractures), muscular weakness, myopathy

Renal and Urinary Disorders
acute renal failure, renal failure, acute tubular necrosis, Fanconi syndrome, proximal renal tubulopathy, interstitial nephritis (including acute cases), nephrogenic diabetes insipidus, renal insufficiency, increased creatinine, proteinuria, polyuria

General Disorders and Administration Site Conditions
asthenia

The following adverse reactions, listed under the body system headings above, may occur as a consequence of proximal renal tubulopathy: rhabdomyolysis, osteomalacia, hypokalemia, muscular weakness, myopathy, hypophosphatemia.

7 DRUG INTERACTIONS

This section describes clinically relevant drug interactions with VIREAD. Drug interactions trials are described elsewhere in the labeling [See Clinical Pharmacology (12.3)].

7.1 Didanosine

Coadministration of VIREAD and didanosine should be undertaken with caution and patients receiving this combination should be monitored closely for didanosine-associated adverse reactions. Didanosine should be discontinued in patients who develop didanosine-associated adverse reactions.

When administered with VIREAD, Cmax and AUC of didanosine increased significantly [See Clinical Pharmacology (12.3)]. The mechanism of this interaction is unknown. Higher didanosine concentrations could potentiate didanosine-associated adverse reactions, including pancreatitis and neuropathy. Suppression of CD4^+ cell counts has been observed in patients receiving VIREAD with didanosine 400 mg daily.

In patients weighing greater than 60 kg, the didanosine dose should be reduced to 250 mg once daily when it is coadministered with VIREAD. In patients weighing less than 60 kg, the didanosine dose should be reduced to 200 mg once daily when it is coadministered with VIREAD. When coadministered, VIREAD and didanosine EC may be taken under fasted conditions or with a light meal (less than 400 kcal, 20% fat). For additional information on coadministration of VIREAD and didanosine, please refer to the full prescribing information for didanosine.

7.2 HIV-1 Protease Inhibitors

VIREAD decreases the AUC and Cmin of atazanavir [See Clinical Pharmacology (12.3)]. When coadministered with VIREAD, it is recommended that atazanavir 300 mg is given with ritonavir 100 mg. VIREAD should not be coadministered with atazanavir without ritonavir.

Lopinavir/ritonavir, atazanavir coadministered with ritonavir, and darunavir coadministered with ritonavir have been shown to increase tenofovir concentrations [See Clinical Pharmacology (12.3)]. Tenofovir disoproxil fumarate is a substrate of P-glycoprotein (Pgp) and breast cancer resistance protein (BCRP) transporters. When tenofovir disoproxil fumarate is coadministered with an inhibitor of these transporters, an increase in absorption may be observed. Patients receiving VIREAD concomitantly with lopinavir/ritonavir, ritonavir-boosted atazanavir, or ritonavir-boosted darunavir should be monitored for VIREAD-associated adverse reactions. VIREAD should be discontinued in patients who develop VIREAD-associated adverse reactions.

7.3 Drugs Affecting Renal Function

Since tenofovir is primarily eliminated by the kidneys [See Clinical Pharmacology (12.3)], coadministration of VIREAD with drugs that reduce renal function or compete for active tubular secretion may increase serum concentrations of tenofovir and/or increase the concentrations of other renally eliminated drugs. Some examples include, but are not limited to, cidofovir, acyclovir, valacyclovir, ganciclovir, valganciclovir, aminoglycosides (e.g., gentamicin), and high-dose or multiple NSAIDs [See Warnings and Precautions (5.3)].

In the treatment of chronic hepatitis B, VIREAD should not be administered in combination with HEPSERA (adefovir dipivoxil).

8 USE IN SPECIFIC POPULATIONS

8.1 Pregnancy

TERATOGENIC EFFECTS

Pregnancy Category B

There are no adequate and well-controlled studies in pregnant women. Because animal reproduction studies are not always predictive of human response, VIREAD should be used during pregnancy only if clearly needed.

Antiretroviral Pregnancy Registry: To monitor fetal outcomes of pregnant women exposed to VIREAD, an Antiretroviral Pregnancy Registry has been established. Healthcare providers are encouraged to register patients by calling 1-800-258-4263.

Animal Data

Reproduction studies have been performed in rats and rabbits at doses up to 14 and 19 times the human dose based on body surface area comparisons and revealed no evidence of impaired fertility or harm to the fetus due to tenofovir.

8.3 Nursing Mothers

Nursing Mothers: The Centers for Disease Control and Prevention recommend that HIV-1-infected mothers not breastfeed their infants to avoid risking postnatal transmission of HIV-1. Samples of breast milk obtained from five HIV-1 infected mothers in the first post-partum week show that tenofovir is secreted in human milk. The impact of this exposure in breastfed infants is unknown. Because of both the potential for HIV-1 transmission and the potential for serious adverse reactions in nursing infants, mothers should be instructed not to breastfeed if they are receiving VIREAD.

8.4 Pediatric Use

Pediatric Patients 2 Years of Age and Older with HIV-1 infection

The safety of VIREAD in pediatric patients aged 2 to less than 18 years is supported by data from two randomized trials in which VIREAD was administered to HIV-1 infected treatment-experienced subjects. In addition, the pharmacokinetic profile of tenofovir in patients 2 to less than 18 years of age at the recommended doses was similar to that found to be safe and effective in adult clinical trials [See Clinical Pharmacology (12.3)].

In Study 352, 92 treatment-experienced subjects 2 to less than 12 years of age with stable, virologic suppression on stavudine- or zidovudine-containing regimen were randomized to either replace stavudine or zidovudine with VIREAD (N = 44) or continue their original regimen (N = 48) for 48 weeks. Five additional subjects over the age of 12 were enrolled and randomized (VIREAD N=4, original regimen N=1) but are not included in the efficacy analysis. After 48 weeks, all eligible subjects were allowed to continue in the study receiving open-label VIREAD. At Week 48, 89% of subjects in the VIREAD treatment group and 90% of subjects in the stavudine or zidovudine treatment group had HIV-1 RNA concentrations less than 400 copies/mL. During the 48 week randomized phase of the study, 1 subject in the VIREAD group discontinued the study prematurely because of virologic failure/lack of efficacy and 3 subjects (2 subjects in the VIREAD group and 1 subject in the stavudine or zidovudine group) discontinued for other reasons.

In Study 321, 87 treatment-experienced subjects 12 to less than 18 years of age were treated with VIREAD (N=45) or placebo (N=42) in combination with an optimized background regimen (OBR) for 48 weeks. The mean baseline CD4 cell count was 374 cells/mm^3 and the mean baseline plasma HIV-1 RNA was 4.6 log10 copies/mL. At baseline, 90% of subjects harbored NRTI resistance-associated substitutions in their HIV-1 isolates. Overall, the trial failed to show a difference in virologic response between the VIREAD and placebo treatment groups. Subgroup analyses suggest the lack of difference in virologic response may be attributable to imbalances between treatment arms in baseline viral susceptibility to VIREAD and OBR.

Although changes in HIV-1 RNA in these highly treatment-experienced subjects were less than anticipated, the comparability of the pharmacokinetic and safety data to that observed in adults supports the use of VIREAD in pediatric patients 12 years of age and older who weigh greater than or equal to 35 kg and whose HIV-1 isolate is expected to be sensitive to VIREAD. [See Warnings and Precautions (5.6), Adverse Reactions (6.1), and Clinical Pharmacology (12.3)].

Safety and effectiveness of VIREAD in pediatric patients younger than 2 years of age with HIV-1 infection have not been established.

Pediatric Patients 12 Years of Age and Older with Chronic Hepatitis B

In Study 115, 106 HBeAg negative (9%) and positive (91%) subjects aged 12 to less than 18 years with chronic HBV infection were randomized to receive blinded treatment with VIREAD 300 mg (N = 52) or placebo (N = 54) for 72 weeks. At study entry, the mean HBV DNA was 8.1 log10 copies/mL and mean ALT was 101 U/L. Of 52 subjects treated with VIREAD, 20 subjects were nucleos(t)ide-naïve and 32 subjects were nucleos(t)ide-experienced. Thirty-one of the 32 nucleos(t)ide-experienced subjects had prior lamivudine experience. At Week 72, 88% (46/52) of subjects in the VIREAD group and 0% (0/54) of subjects in the placebo group had HBV DNA <400 copies/mL (69 IU/mL). Among subjects with abnormal ALT at baseline, 74% (26/35) of subjects receiving VIREAD had normalized ALT at Week 72 compared to 31% (13/42) in the placebo group. One VIREAD-treated subject experienced sustained HBsAg-loss and seroconversion to anti-HBs during the first 72 weeks of study participation.

Safety and effectiveness of VIREAD in pediatric patients younger than 12 years of age or less than 35 kg with chronic hepatitis B have not been established.

8.5 Geriatric Use

Clinical trials of VIREAD did not include sufficient numbers of subjects aged 65 and over to determine whether they respond differently from younger subjects. In general, dose selection for the elderly patient should be cautious, keeping in mind the greater frequency of decreased hepatic, renal, or cardiac function, and of concomitant disease or other drug therapy.

8.6 Patients with Impaired Renal Function

It is recommended that the dosing interval for VIREAD be modified in patients with estimated creatinine clearance below 50 mL/min or in patients with ESRD who require dialysis [See Dosage and Administration (2.3), Clinical Pharmacology (12.3)].

10 OVERDOSAGE

Limited clinical experience at doses higher than the therapeutic dose of VIREAD 300 mg is available. In Study 901, 600 mg tenofovir disoproxil fumarate was administered to 8 subjects orally for 28 days. No severe adverse reactions were reported. The effects of higher doses are not known.

If overdose occurs the patient must be monitored for evidence of toxicity, and standard supportive treatment applied as necessary.

Tenofovir is efficiently removed by hemodialysis with an extraction coefficient of approximately 54%. Following a single 300 mg dose of VIREAD, a four-hour hemodialysis session removed approximately 10% of the administered tenofovir dose.

11 DESCRIPTION

VIREAD is the brand name for tenofovir disoproxil fumarate (a prodrug of tenofovir) which is a fumaric acid salt of bis-isopropoxycarbonyloxymethyl ester derivative of tenofovir. In vivo tenofovir disoproxil fumarate is converted to tenofovir, an acyclic nucleoside phosphonate (nucleotide) analog of adenosine 5'-monophosphate. Tenofovir exhibits activity against HIV-1 reverse transcriptase.

The chemical name of tenofovir disoproxil fumarate is 9-[(R)-2-[[bis[[(isopropoxycarbonyl)oxy]methoxy]phosphinyl]methoxy]propyl]adenine fumarate (1:1). It has a molecular formula of C19H30N5O10P • C4H4O4 and a molecular weight of 635.52. It has the following structural formula:

Tenofovir disoproxil fumarate is a white to off-white crystalline powder with a solubility of 13.4 mg/mL in distilled water at 25 °C. It has an octanol/phosphate buffer (pH 6.5) partition coefficient (log p) of 1.25 at 25 °C.

VIREAD is available as tablets or as an oral powder.

VIREAD tablets are for oral administration in strengths of 150, 200, 250, and 300 mg of tenofovir disoproxil fumarate, which are equivalent to 123, 163, 204 and 245 mg of tenofovir disoproxil, respectively. Each tablet contains the following inactive ingredients: croscarmellose sodium, lactose monohydrate, magnesium stearate, microcrystalline cellulose, and pregelatinized starch. The 300 mg tablets are coated with Opadry II Y-30-10671-A, which contains FD&C blue #2 aluminum lake, hypromellose 2910, lactose monohydrate, titanium dioxide, and triacetin. The 150, 200, and 250 mg tablets are coated with Opadry II 32K-18425, which contains hypromellose 2910, lactose monohydrate, titanium dioxide, and triacetin.

VIREAD oral powder is available for oral administration as white, taste-masked, coated granules containing 40 mg of tenofovir disoproxil fumarate per gram of oral powder, which is equivalent to 33 mg of tenofovir disoproxil. The oral powder contains the following inactive ingredients: mannitol, hydroxypropyl cellulose, ethylcellulose, and silicon dioxide.

In this insert, all dosages are expressed in terms of tenofovir disoproxil fumarate except where otherwise noted.

12 CLINICAL PHARMACOLOGY

12.1 Mechanism of Action

Tenofovir disoproxil fumarate is an antiviral drug [See Microbiology (12.4)].

12.3 Pharmacokinetics

The pharmacokinetics of tenofovir disoproxil fumarate have been evaluated in healthy volunteers and HIV-1 infected individuals. Tenofovir pharmacokinetics are similar between these populations.

Absorption

VIREAD is a water soluble diester prodrug of the active ingredient tenofovir. The oral bioavailability of tenofovir from VIREAD in fasted subjects is approximately 25%. Following oral administration of a single dose of VIREAD 300 mg to HIV-1 infected subjects in the fasted state, maximum serum concentrations (Cmax) are achieved in 1.0 ± 0.4 hrs. Cmax and AUC values are 0.30 ± 0.09 µg/mL and 2.29 ± 0.69 µg∙hr/mL, respectively.

The pharmacokinetics of tenofovir are dose proportional over a VIREAD dose range of 75 to 600 mg and are not affected by repeated dosing.

In a single-dose bioequivalence study conducted under non-fasted conditions (dose administered with 4 oz. applesauce) in healthy adult volunteers, the mean Cmax of tenofovir was 26% lower for the oral powder relative to the tablet formulation. Mean AUC of tenofovir was similar between the oral powder and tablet formulations.

Distribution

In vitro binding of tenofovir to human plasma or serum proteins is less than 0.7 and 7.2%, respectively, over the tenofovir concentration range 0.01 to 25 µg/mL. The volume of distribution at steady-state is 1.3 ± 0.6 L/kg and 1.2 ± 0.4 L/kg, following intravenous administration of tenofovir 1.0 mg/kg and 3.0 mg/kg.

Metabolism and Elimination

In vitro studies indicate that neither tenofovir disoproxil nor tenofovir are substrates of CYP enzymes.

Following IV administration of tenofovir, approximately 70–80% of the dose is recovered in the urine as unchanged tenofovir within 72 hours of dosing. Following single dose, oral administration of VIREAD, the terminal elimination half-life of tenofovir is approximately 17 hours. After multiple oral doses of VIREAD 300 mg once daily (under fed conditions), 32 ± 10% of the administered dose is recovered in urine over 24 hours.

Tenofovir is eliminated by a combination of glomerular filtration and active tubular secretion. There may be competition for elimination with other compounds that are also renally eliminated.

Effects of Food on Oral Absorption

Administration of VIREAD 300 mg tablets following a high-fat meal (~700 to 1000 kcal containing 40 to 50% fat) increases the oral bioavailability, with an increase in tenofovir AUC0–∞ of approximately 40% and an increase in Cmax of approximately 14%. However, administration of VIREAD with a light meal did not have a significant effect on the pharmacokinetics of tenofovir when compared to fasted administration of the drug. Food delays the time to tenofovir Cmax by approximately 1 hour. Cmax and AUC of tenofovir are 0.33 ± 0.12 µg/mL and 3.32 ± 1.37 µg∙hr/mL following multiple doses of VIREAD 300 mg once daily in the fed state, when meal content was not controlled.

Special Populations

Race: There were insufficient numbers from racial and ethnic groups other than Caucasian to adequately determine potential pharmacokinetic differences among these populations.

Gender: Tenofovir pharmacokinetics are similar in male and female subjects.

Pediatric Patients 2 Years of Age and Older: Steady-state pharmacokinetics of tenofovir were evaluated in 31 HIV-1 infected pediatric subjects 2 to less than 18 years (Table 11). Tenofovir exposure achieved in these pediatric subjects receiving oral once daily doses of VIREAD 300 mg (tablet) or 8 mg/kg of body weight (powder) up to a maximum dose of 300 mg was similar to exposures achieved in adults receiving once-daily doses of VIREAD 300 mg.

Table 11 Mean (± SD) Tenofovir Pharmacokinetic Parameters by Age Groups for HIV-1-infected Pediatric Patients
Dose and Formulation | 300 mg Tablet | 8 mg/kg Oral Powder
 | 12 to <18 Years (N=8) | 2 to <12 Years (N=23)
Cmax (µg/mL) | 0.38 ± 0.13 | 0.24 ± 0.13
AUCtau (µg∙hr/mL) | 3.39 ± 1.22 | 2.59 ± 1.06

Tenofovir exposures in 52 HBV-infected pediatric subjects (12 to less than 18 years of age) receiving oral once-daily doses of VIREAD 300 mg tablet were comparable to exposures achieved in HIV-1-infected adults and adolescents receiving once-daily doses of 300 mg.

Geriatric Patients: Pharmacokinetic trials have not been performed in the elderly (65 years and older).

Patients with Impaired Renal Function: The pharmacokinetics of tenofovir are altered in subjects with renal impairment [See Warnings and Precautions (5.3)]. In subjects with creatinine clearance below 50 mL/min or with end-stage renal disease (ESRD) requiring dialysis, Cmax, and AUC0–∞ of tenofovir were increased (Table 12). It is recommended that the dosing interval for VIREAD be modified in patients with estimated creatinine clearance below 50 mL/min or in patients with ESRD who require dialysis [See Dosage and Administration (2.3)].

Table 12 Pharmacokinetic Parameters (Mean ± SD) of Tenofovir [300 mg, single dose of VIREAD] in Subjects with Varying Degrees of Renal Function
Baseline Creatinine Clearance (mL/min) | >80 (N=3) | 50–80 (N=10) | 30–49 (N=8) | 12–29 (N=11)
Cmax (µg/mL) | 0.34 ± 0.03 | 0.33 ± 0.06 | 0.37 ± 0.16 | 0.60 ± 0.19
AUC0–∞ (µg∙hr/mL) | 2.18 ± 0.26 | 3.06 ± 0.93 | 6.01 ± 2.50 | 15.98 ± 7.22
CL/F (mL/min) | 1043.7 ± 115.4 | 807.7 ± 279.2 | 444.4 ± 209.8 | 177.0 ± 97.1
CLrenal (mL/min) | 243.5 ± 33.3 | 168.6 ± 27.5 | 100.6 ± 27.5 | 43.0 ± 31.2

Tenofovir is efficiently removed by hemodialysis with an extraction coefficient of approximately 54%. Following a single 300 mg dose of VIREAD, a four-hour hemodialysis session removed approximately 10% of the administered tenofovir dose.

Patients with Hepatic Impairment: The pharmacokinetics of tenofovir following a 300 mg single dose of VIREAD have been studied in non-HIV infected subjects with moderate to severe hepatic impairment. There were no substantial alterations in tenofovir pharmacokinetics in subjects with hepatic impairment compared with unimpaired subjects. No change in VIREAD dosing is required in patients with hepatic impairment.

Assessment of Drug Interactions

At concentrations substantially higher (~300-fold) than those observed in vivo, tenofovir did not inhibit in vitro drug metabolism mediated by any of the following human CYP isoforms: CYP3A4, CYP2D6, CYP2C9, or CYP2E1. However, a small (6%) but statistically significant reduction in metabolism of CYP1A substrate was observed. Based on the results of in vitro experiments and the known elimination pathway of tenofovir, the potential for CYP mediated interactions involving tenofovir with other medicinal products is low.

VIREAD has been evaluated in healthy volunteers in combination with other antiretroviral and potential concomitant drugs. Tables 13 and 14 summarize pharmacokinetic effects of coadministered drug on tenofovir pharmacokinetics and effects of VIREAD on the pharmacokinetics of coadministered drug. Coadministration of VIREAD with didanosine results in changes in the pharmacokinetics of didanosine that may be of clinical significance. Concomitant dosing of VIREAD with didanosine significantly increases the Cmax and AUC of didanosine. When didanosine 250 mg enteric-coated capsules were administered with VIREAD, systemic exposures of didanosine were similar to those seen with the 400 mg enteric-coated capsules alone under fasted conditions (Table 14). The mechanism of this interaction is unknown.

No clinically significant drug interactions have been observed between VIREAD and efavirenz, methadone, nelfinavir, oral contraceptives, or ribavirin.

Table 13 Drug Interactions: Changes in Pharmacokinetic Parameters for Tenofovir [Subjects received VIREAD 300 mg once daily.] in the Presence of the Coadministered Drug
Coadministered Drug | Dose of Coadministered Drug (mg) | N | % Change of Tenofovir Pharmacokinetic Parameters [Increase = ↑; Decrease = ↓; No Effect = ; NC = Not Calculated] (90% CI)
Coadministered Drug | Dose of Coadministered Drug (mg) | N | Cmax | AUC | Cmin
Abacavir | 300 once | 8 |  |  | NC
Atazanavir [Reyataz Prescribing Information] | 400 once daily × 14 days | 33 | ↑ 14 (↑ 8 to ↑ 20) | ↑ 24 (↑ 21 to ↑ 28) | ↑ 22 (↑ 15 to ↑ 30)
Atazanavir/ Ritonavir | 300/100 once daily | 12 | ↑ 34 (↑ 20 to ↑ 51) | ↑ 37 (↑ 30 to ↑ 45) | ↑ 29 (↑ 21 to ↑ 36)
Darunavir/ Ritonavir [Prezista Prescribing Information] | 300/100 twice daily | 12 | ↑ 24 (↑ 8 to ↑ 42) | ↑ 22 (↑ 10 to ↑ 35) | ↑ 37 (↑ 19 to ↑ 57)
Didanosine [Subjects received didanosine buffered tablets.] | 250 or 400 once daily × 7 days | 14
Emtricitabine | 200 once daily × 7 days | 17
Entecavir | 1 mg once daily × 10 days | 28
Indinavir | 800 three times daily × 7 days | 13 | ↑ 14 (↓ 3 to ↑ 33)
Lamivudine | 150 twice daily × 7 days | 15
Lopinavir/Ritonavir | 400/100 twice daily × 14 days | 24 |  | ↑ 32 (↑ 25 to ↑ 38) | ↑ 51 (↑ 37 to ↑ 66)
Saquinavir/Ritonavir | 1000/100 twice daily × 14 days | 35 |  |  | ↑ 23 (↑ 16 to ↑ 30)
Tacrolimus | 0.05 mg/kg twice daily × 7 days | 21 | ↑ 13 (↑ 1 to ↑ 27)
Tipranavir/ Ritonavir [Aptivus Prescribing Information] | 500/100 twice daily | 22 | ↓ 23 (↓ 32 to ↓ 13) | ↓ 2 (↓ 9 to ↑ 5) | ↑ 7 (↓ 2 to ↑ 17)
Tipranavir/ Ritonavir [Aptivus Prescribing Information] | 750/200 twice daily (23 doses) | 20 | ↓ 38 (↓ 46 to ↓ 29) | ↑ 2 (↓ 6 to ↑ 10) | ↑ 14 (↑ 1 to ↑ 27)

Table 14 Drug Interactions: Changes in Pharmacokinetic Parameters for Coadministered Drug in the Presence of VIREAD
Coadministered Drug | Dose of Coadministered Drug (mg) | N | % Change of Coadministered Drug Pharmacokinetic Parameters [Increase = ↑; Decrease = ↓; No Effect = ; NA = Not Applicable] (90% CI)
Coadministered Drug | Dose of Coadministered Drug (mg) | N | Cmax | AUC | Cmin
Abacavir | 300 once | 8 | ↑ 12 (↓ 1 to ↑ 26) |  | NA
Atazanavir [Reyataz Prescribing Information] | 400 once daily × 14 days | 34 | ↓ 21 (↓ 27 to ↓ 14) | ↓ 25 (↓ 30 to ↓ 19) | ↓ 40 (↓ 48 to ↓ 32)
Atazanavir | Atazanavir/ Ritonavir 300/100 once daily × 42 days | 10 | ↓ 28 (↓ 50 to ↑ 5) | ↓ 25 [In HIV-infected subjects, addition of tenofovir DF to atazanavir 300 mg plus ritonavir 100 mg, resulted in AUC and Cmin values of atazanavir that were 2.3- and 4-fold higher than the respective values observed for atazanavir 400 mg when given alone.] (↓ 42 to ↓ 3) | ↓ 23 (↓ 46 to ↑ 10)
Darunavir [Prezista Prescribing Information] | Darunavir/Ritonavir 300/100 mg once daily | 12 | ↑ 16 (↓ 6 to ↑ 42) | ↑ 21 (↓ 5 to ↑ 54) | ↑ 24 (↓ 10 to ↑ 69)
Didanosine [Videx EC Prescribing Information. Subjects received didanosine enteric-coated capsules.] | 250 once, simultaneously with VIREAD and a light meal [373 kcal, 8.2 g fat] | 33 | ↓ 20 [Compared with didanosine (enteric-coated) 400 mg administered alone under fasting conditions.] (↓ 32 to ↓ 7) |  | NA
Emtricitabine | 200 once daily × 7 days | 17 |  |  | ↑ 20 (↑ 12 to ↑ 29)
Entecavir | 1 mg once daily × 10 days | 28 |  | ↑ 13 (↑ 11 to ↑ 15)
Indinavir | 800 three times daily × 7 days | 12 | ↓ 11 (↓ 30 to ↑ 12)
Lamivudine | 150 twice daily × 7 days | 15 | ↓ 24 (↓ 34 to ↓ 12)
Lopinavir | Lopinavir/Ritonavir 400/100 twice daily × 14 days | 24
Ritonavir | Lopinavir/Ritonavir 400/100 twice daily × 14 days | 24
Saquinavir | Saquinavir/Ritonavir 1000/100 twice daily × 14 days | 32 | ↑ 22 (↑ 6 to ↑ 41) | ↑ 29 [Increases in AUC and Cmin are not expected to be clinically relevant; hence no dose adjustments are required when tenofovir DF and ritonavir-boosted saquinavir are coadministered.] (↑ 12 to ↑ 48) | ↑ 47 (↑ 23 to ↑ 76)
Ritonavir | Saquinavir/Ritonavir 1000/100 twice daily × 14 days | 32 |  |  | ↑ 23 (↑ 3 to ↑ 46)
Tacrolimus | 0.05 mg/kg twice daily × 7 days | 21
Tipranavir [Aptivus Prescribing Information] | Tipranavir/Ritonavir 500/100 twice daily | 22 | ↓ 17 (↓ 26 to ↓ 6) | ↓ 18 (↓ 25 to ↓ 9) | ↓ 21 (↓ 30 to ↓ 10)
Tipranavir [Aptivus Prescribing Information] | Tipranavir/Ritonavir 750/200 twice daily (23 doses) | 20 | ↓ 11 (↓ 16 to ↓ 4) | ↓ 9 (↓ 15 to ↓ 3) | ↓ 12 (↓ 22 to 0)

12.4 Microbiology

Mechanism of Action

Tenofovir disoproxil fumarate is an acyclic nucleoside phosphonate diester analog of adenosine monophosphate. Tenofovir disoproxil fumarate requires initial diester hydrolysis for conversion to tenofovir and subsequent phosphorylations by cellular enzymes to form tenofovir diphosphate, an obligate chain terminator. Tenofovir diphosphate inhibits the activity of HIV-1 reverse transcriptase and HBV reverse transcriptase by competing with the natural substrate deoxyadenosine 5'-triphosphate and, after incorporation into DNA, by DNA chain termination. Tenofovir diphosphate is a weak inhibitor of mammalian DNA polymerases α, β, and mitochondrial DNA polymerase γ.

Activity against HIV

Antiviral Activity

The antiviral activity of tenofovir against laboratory and clinical isolates of HIV-1 was assessed in lymphoblastoid cell lines, primary monocyte/macrophage cells and peripheral blood lymphocytes. The EC50 (50% effective concentration) values for tenofovir were in the range of 0.04 µM to 8.5 µM. In drug combination studies, tenofovir was not antagonistic with nucleoside reverse transcriptase inhibitors (abacavir, didanosine, lamivudine, stavudine, zalcitabine, zidovudine), non-nucleoside reverse transcriptase inhibitors (delavirdine, efavirenz, nevirapine), and protease inhibitors (amprenavir, indinavir, nelfinavir, ritonavir, saquinavir). Tenofovir displayed antiviral activity in cell culture against HIV-1 clades A, B, C, D, E, F, G, and O (EC50 values ranged from 0.5 µM to 2.2 µM) and strain specific activity against HIV-2 (EC50 values ranged from 1.6 µM to 5.5 µM).

Resistance

HIV-1 isolates with reduced susceptibility to tenofovir have been selected in cell culture. These viruses expressed a K65R substitution in reverse transcriptase and showed a 2- to 4- fold reduction in susceptibility to tenofovir.

In Study 903 of treatment-naïve subjects (VIREAD + lamivudine + efavirenz versus stavudine + lamivudine + efavirenz) [See Clinical Studies (14.1)], genotypic analyses of isolates from subjects with virologic failure through Week 144 showed development of efavirenz and lamivudine resistance-associated substitutions to occur most frequently and with no difference between the treatment arms. The K65R substitution occurred in 8/47 (17%) analyzed patient isolates on the VIREAD arm and in 2/49 (4%) analyzed patient isolates on the stavudine arm. Of the 8 subjects whose virus developed K65R in the VIREAD arm through 144 weeks, 7 of these occurred in the first 48 weeks of treatment and one at Week 96. Other substitutions resulting in resistance to VIREAD were not identified in this trial.

In Study 934 of treatment-naïve subjects (VIREAD + EMTRIVA + efavirenz versus zidovudine (AZT)/lamivudine (3TC) + efavirenz) [See Clinical Studies (14.1)], genotypic analysis performed on HIV-1 isolates from all confirmed virologic failure subjects with greater than 400 copies/mL of HIV-1 RNA at Week 144 or early discontinuation showed development of efavirenz resistance-associated substitutions occurred most frequently and was similar between the two treatment arms. The M184V substitution, associated with resistance to EMTRIVA and lamivudine, was observed in 2/19 analyzed subject isolates in the VIREAD + EMTRIVA group and in 10/29 analyzed subject isolates in the zidovudine/lamivudine group. Through 144 weeks of Study 934, no subjects have developed a detectable K65R substitution in their HIV-1 as analyzed through standard genotypic analysis.

Cross-Resistance

Cross-resistance among certain reverse transcriptase inhibitors has been recognized. The K65R substitution selected by tenofovir is also selected in some HIV-1 infected subjects treated with abacavir, didanosine, or zalcitabine. HIV-1 isolates with this substitution also show reduced susceptibility to emtricitabine and lamivudine. Therefore, cross-resistance among these drugs may occur in patients whose virus harbors the K65R substitution. HIV-1 isolates from subjects (N=20) whose HIV-1 expressed a mean of 3 zidovudine-associated reverse transcriptase substitutions (M41L, D67N, K70R, L210W, T215Y/F, or K219Q/E/N), showed a 3.1-fold decrease in the susceptibility to tenofovir.

In Studies 902 and 907 conducted in treatment-experienced subjects (VIREAD + Standard Background Therapy (SBT) compared to Placebo + SBT) [See Clinical Studies (14.1)], 14/304 (5%) of the VIREAD-treated subjects with virologic failure through Week 96 had greater than 1.4-fold (median 2.7-fold) reduced susceptibility to tenofovir. Genotypic analysis of the baseline and failure isolates showed the development of the K65R substitution in the HIV-1 reverse transcriptase gene.

The virologic response to VIREAD therapy has been evaluated with respect to baseline viral genotype (N=222) in treatment-experienced subjects participating in Studies 902 and 907. In these clinical trials, 94% of the participants evaluated had baseline HIV-1 isolates expressing at least one NRTI substitution. Virologic responses for subjects in the genotype substudy were similar to the overall trial results.

Several exploratory analyses were conducted to evaluate the effect of specific substitutions and substitutional patterns on virologic outcome. Because of the large number of potential comparisons, statistical testing was not conducted. Varying degrees of cross-resistance of VIREAD to pre-existing zidovudine resistance-associated substitutions (M41L, D67N, K70R, L210W, T215Y/F, or K219Q/E/N) were observed and appeared to depend on the type and number of specific substitutions. VIREAD-treated subjects whose HIV-1 expressed 3 or more zidovudine resistance-associated substitutions that included either the M41L or L210W reverse transcriptase substitution showed reduced responses to VIREAD therapy; however, these responses were still improved compared with placebo. The presence of the D67N, K70R, T215Y/F, or K219Q/E/N substitution did not appear to affect responses to VIREAD therapy. Subjects whose virus expressed an L74V substitution without zidovudine resistance associated substitutions (N=8) had reduced response to VIREAD. Limited data are available for subjects whose virus expressed a Y115F substitution (N=3), Q151M substitution (N=2), or T69 insertion (N=4), all of whom had a reduced response.

In the protocol defined analyses, virologic response to VIREAD was not reduced in subjects with HIV-1 that expressed the abacavir/emtricitabine/lamivudine resistance-associated M184V substitution. HIV-1 RNA responses among these subjects were durable through Week 48.

Studies 902 and 907 Phenotypic Analyses

Phenotypic analysis of baseline HIV-1 from treatment-experienced subjects (N=100) demonstrated a correlation between baseline susceptibility to VIREAD and response to VIREAD therapy. Table 15 summarizes the HIV-1 RNA response by baseline VIREAD susceptibility.

Table 15 HIV-1 RNA Response at Week 24 by Baseline VIREAD Susceptibility (Intent-To-Treat) [Tenofovir susceptibility was determined by recombinant phenotypic Antivirogram assay (Virco).]
Baseline VIREAD Susceptibility [Fold change in susceptibility from wild-type.] | Change in HIV-1 RNA [Average HIV-1 RNA change from baseline through Week 24 (DAVG24) in log10 copies/mL.] (N)
<1 | -0.74 (35)
>1 and ≤3 | -0.56 (49)
>3 and ≤4 | -0.3 (7)
>4 | -0.12 (9)

Activity against HBV

Antiviral Activity

The antiviral activity of tenofovir against HBV was assessed in the HepG2 2.2.15 cell line. The EC50 values for tenofovir ranged from 0.14 to 1.5 µM, with CC50 (50% cytotoxicity concentration) values greater than 100 µM. In cell culture combination antiviral activity studies of tenofovir with the nucleoside HBV reverse transcriptase inhibitors entecavir, lamivudine, and telbivudine, and with the nucleoside HIV-1 reverse transcriptase inhibitor emtricitabine, no antagonistic activity was observed.

Resistance

Cumulative VIREAD genotypic resistance has been evaluated annually for up to 384 weeks in Studies 0102, 0103, 0106, 0108, and 0121 with the paired HBV reverse transcriptase amino acid sequences of the pre-treatment and on-treatment isolates from subjects who received at least 24 weeks of VIREAD monotherapy and remained viremic with HBV DNA greater than or equal to 400 copies/mL (69 IU/mL) at the end of each study year (or at discontinuation of VIREAD monotherapy) using an as-treated analysis. In the nucleotide-naïve population from Studies 0102 and 0103, HBeAg-positive subjects had a higher baseline viral load than HBeAg-negative subjects and a significantly higher proportion of the subjects remained viremic at their last time point on VIREAD monotherapy (15% versus 5%, respectively).

HBV isolates from these subjects who remained viremic showed treatment-emergent substitutions (Table 16); however, no specific substitutions occurred at a sufficient frequency to be associated with resistance to VIREAD (genotypic and phenotypic analyses).

Table 16 Amino Acid Substitutions in Viremic Subjects Across HBV Trials of VIREAD
 | Compensated Liver Disease |  |  | Decompensated Liver Disease (N=39) [Subjects with decompensated liver disease from Study 0108 (N=39) receiving up to 48 weeks of treatment with VIREAD.]
 | Nucleotide-Naïve (N=417) [Nucleotide-naïve subjects from Studies 0102 (N=246) and 0103 (N=171) receiving up to 384 weeks of treatment with VIREAD.] | HEPSERA-Experienced (N=247) [HEPSERA-experienced subjects from Studies 0102/0103 (N=195) and 0106 (N=52) receiving up to 336 weeks of treatment with VIREAD after switching to VIREAD from HEPSERA. Study 0106, a randomized, double-blind, 168-week Phase 2 trial, has been completed.] | Lamivudine- Resistant (N=136) [Lamivudine-resistant subjects from Study 0121 (N=136) receiving up to 96 weeks of treatment with VIREAD after switching to VIREAD from lamivudine.] | Decompensated Liver Disease (N=39) [Subjects with decompensated liver disease from Study 0108 (N=39) receiving up to 48 weeks of treatment with VIREAD.]
Viremic at Last Time Point on VIREAD | 38/417 (9%) | 37/247 (15%) | 9/136 (7%) | 7/39 (18%)
Treatment-Emergent Amino Acid Substitutions [Denominator includes those subjects who were viremic at last time point on VIREAD monotherapy and had evaluable paired genotypic data.] | 18 [Of the 18 subjects with treatment-emergent amino acid substitutions during Studies 0102 and 0103, 5 subjects had substitutions at conserved sites and 13 subjects had substitutions only at polymorphic sites, and 8 subjects had only transient substitutions that were not detected at the last time point on VIREAD.] /32 (56%) | 11 [Of the 11 HEPSERA-experienced subjects with treatment-emergent amino acid substitutions, 2 subjects had substitutions at conserved sites and 9 had substitutions only at polymorphic sites.] /31 (35%) | 6 [Of the 6 lamivudine-resistant subjects with treatment-emergent substitutions during Study 0121, 3 subjects had substitutions at conserved sites and 3 had substitutions only at polymorphic sites.] /8 (75%) | 3/5 (60%)

Cross-Resistance

Cross-resistance has been observed between HBV nucleoside/nucleotide analogue reverse transcriptase inhibitors.

In cell based assays, HBV strains expressing the rtV173L, rtL180M, and rtM204I/V substitutions associated with resistance to lamivudine and telbivudine showed a susceptibility to tenofovir ranging from 0.7- to 3.4-fold that of wild type virus. The rtL180M and rtM204I/V double substitutions conferred 3.4-fold reduced susceptibility to tenofovir.

HBV strains expressing the rtL180M, rtT184G, rtS202G/I, rtM204V, and rtM250V substitutions associated with resistance to entecavir showed a susceptibility to tenofovir ranging from 0.6- to 6.9-fold that of wild type virus.

HBV strains expressing the adefovir resistance-associated substitutions rtA181V and/or rtN236T showed reductions in susceptibility to tenofovir ranging from 2.9- to 10-fold that of wild type virus. Strains containing the rtA181T substitution showed changes in susceptibility to tenofovir ranging from 0.9- to 1.5-fold that of wild type virus.

One hundred fifty-two subjects initiating VIREAD therapy in Studies 0102, 0103, 0106, 0108, and 0121 harbored HBV with known resistance substitutions to HBV nucleos(t)ide analogue reverse transcriptase inhibitors: 14 with adefovir resistance-associated substitutions (rtA181S/T/V and/or rtN236T), 135 with lamivudine resistance-associated substitutions (rtM204I/V), and 3 with both adefovir and lamivudine resistance-associated substitutions. Following up to 384 weeks of VIREAD treatment, 10 of the 14 subjects with adefovir-resistant HBV, 124 of the 135 subjects with lamivudine-resistant HBV, and 2 of the 3 subjects with both adefovir- and lamivudine-resistant HBV achieved and maintained virologic suppression (HBV DNA less than 400 copies/mL [69 IU/mL]). Three of the 5 subjects whose virus harbored both the rtA181T/V and rtN236T substitutions remained viremic.

13 NONCLINICAL TOXICOLOGY

13.1 Carcinogenesis, Mutagenesis, Impairment of Fertility

Carcinogenesis

Long-term oral carcinogenicity studies of tenofovir disoproxil fumarate in mice and rats were carried out at exposures up to approximately 16 times (mice) and 5 times (rats) those observed in humans at the therapeutic dose for HIV-1 infection. At the high dose in female mice, liver adenomas were increased at exposures 16 times that in humans. In rats, the study was negative for carcinogenic findings at exposures up to 5 times that observed in humans at the therapeutic dose.

Mutagenesis

Tenofovir disoproxil fumarate was mutagenic in the in vitro mouse lymphoma assay and negative in an in vitro bacterial mutagenicity test (Ames test). In an in vivo mouse micronucleus assay, tenofovir disoproxil fumarate was negative when administered to male mice.

Impairment of Fertility

There were no effects on fertility, mating performance or early embryonic development when tenofovir disoproxil fumarate was administered to male rats at a dose equivalent to 10 times the human dose based on body surface area comparisons for 28 days prior to mating and to female rats for 15 days prior to mating through day seven of gestation. There was, however, an alteration of the estrous cycle in female rats.

13.2 Animal Toxicology and/or Pharmacology

Tenofovir and tenofovir disoproxil fumarate administered in toxicology studies to rats, dogs, and monkeys at exposures (based on AUCs) greater than or equal to 6 fold those observed in humans caused bone toxicity. In monkeys the bone toxicity was diagnosed as osteomalacia. Osteomalacia observed in monkeys appeared to be reversible upon dose reduction or discontinuation of tenofovir. In rats and dogs, the bone toxicity manifested as reduced bone mineral density. The mechanism(s) underlying bone toxicity is unknown.

Evidence of renal toxicity was noted in 4 animal species. Increases in serum creatinine, BUN, glycosuria, proteinuria, phosphaturia, and/or calciuria and decreases in serum phosphate were observed to varying degrees in these animals. These toxicities were noted at exposures (based on AUCs) 2–20 times higher than those observed in humans. The relationship of the renal abnormalities, particularly the phosphaturia, to the bone toxicity is not known.

14 CLINICAL STUDIES

14.1 Clinical Efficacy in Adults with HIV-1 Infection

Treatment-Naïve Adult Patients

Study 903

Data through 144 weeks are reported for Study 903, a double-blind, active-controlled multicenter trial comparing VIREAD (300 mg once daily) administered in combination with lamivudine and efavirenz versus stavudine (d4T), lamivudine, and efavirenz in 600 antiretroviral-naïve subjects. Subjects had a mean age of 36 years (range 18–64), 74% were male, 64% were Caucasian and 20% were Black. The mean baseline CD4^+ cell count was 279 cells/mm^3 (range 3–956) and median baseline plasma HIV-1 RNA was 77,600 copies/mL (range 417–5,130,000). Subjects were stratified by baseline HIV-1 RNA and CD4^+ cell count. Forty-three percent of subjects had baseline viral loads >100,000 copies/mL and 39% had CD4^+ cell counts <200 cells/mm^3. Treatment outcomes through 48 and 144 weeks are presented in Table 17.

Table 17 Outcomes of Randomized Treatment at Week 48 and 144 (Study 903)
 | At Week 48 |  | At Week 144
Outcomes | VIREAD+3TC +EFV (N=299) | d4T+3TC +EFV (N=301) | VIREAD+3TC +EFV (N=299) | d4T+3TC +EFV (N=301)
Responder [Subjects achieved and maintained confirmed HIV-1 RNA <400 copies/mL through Week 48 and 144.] | 79% | 82% | 68% | 62%
Virologic failure [Includes confirmed viral rebound and failure to achieve confirmed <400 copies/mL through Week 48 and 144.] | 6% | 4% | 10% | 8%
Rebound | 5% | 3% | 8% | 7%
Never suppressed | 0% | 1% | 0% | 0%
Added an antiretroviral agent | 1% | 1% | 2% | 1%
Death | <1% | 1% | <1% | 2%
Discontinued due to adverse event | 6% | 6% | 8% | 13%
Discontinued for other reasons [Includes lost to follow-up, subject's withdrawal, noncompliance, protocol violation and other reasons.] | 8% | 7% | 14% | 15%

Achievement of plasma HIV-1 RNA concentrations of less than 400 copies/mL at Week 144 was similar between the two treatment groups for the population stratified at baseline on the basis of HIV-1 RNA concentration (> or ≤100,000 copies/mL) and CD4^+ cell count (< or ≥200 cells/mm^3). Through 144 weeks of therapy, 62% and 58% of subjects in the VIREAD and stavudine arms, respectively achieved and maintained confirmed HIV-1 RNA <50 copies/mL. The mean increase from baseline in CD4^+ cell count was 263 cells/mm^3 for the VIREAD arm and 283 cells/mm^3 for the stavudine arm.

Through 144 weeks, 11 subjects in the VIREAD group and 9 subjects in the stavudine group experienced a new CDC Class C event.

Study 934

Data through 144 weeks are reported for Study 934, a randomized, open-label, active-controlled multicenter trial comparing emtricitabine + VIREAD administered in combination with efavirenz versus zidovudine/lamivudine fixed-dose combination administered in combination with efavirenz in 511 antiretroviral-naïve subjects. From Weeks 96 to 144 of the trial, subjects received a fixed-dose combination of emtricitabine and tenofovir DF with efavirenz in place of emtricitabine + VIREAD with efavirenz. Subjects had a mean age of 38 years (range 18–80), 86% were male, 59% were Caucasian and 23% were Black. The mean baseline CD4^+ cell count was 245 cells/mm^3 (range 2–1191) and median baseline plasma HIV-1 RNA was 5.01 log10 copies/mL (range 3.56–6.54). Subjects were stratified by baseline CD4^+ cell count (< or ≥200 cells/mm^3); 41% had CD4^+ cell counts <200 cells/mm^3 and 51% of subjects had baseline viral loads >100,000 copies/mL. Treatment outcomes through 48 and 144 weeks for those subjects who did not have efavirenz resistance at baseline are presented in Table 18.

Table 18 Outcomes of Randomized Treatment at Week 48 and 144 (Study 934)
Outcomes | At Week 48 |  | At Week 144
Outcomes | FTC +VIREAD +EFV (N=244) | AZT/3TC +EFV (N=243) | FTC +VIREAD +EFV (N=227) [Subjects who were responders at Week 48 or Week 96 (HIV-1 RNA <400 copies/mL) but did not consent to continue the trial after Week 48 or Week 96 were excluded from analysis.] | AZT/3TC +EFV (N=229)
Responder [Subjects achieved and maintained confirmed HIV-1 RNA <400 copies/mL through Weeks 48 and 144.] | 84% | 73% | 71% | 58%
Virologic failure [Includes confirmed viral rebound and failure to achieve confirmed <400 copies/mL through Weeks 48 and 144.] | 2% | 4% | 3% | 6%
Rebound | 1% | 3% | 2% | 5%
Never suppressed | 0% | 0% | 0% | 0%
Change in antiretroviral regimen | 1% | 1% | 1% | 1%
Death | <1% | 1% | 1% | 1%
Discontinued due to adverse event | 4% | 9% | 5% | 12%
Discontinued for other reasons [Includes lost to follow-up, subject withdrawal, noncompliance, protocol violation and other reasons.] | 10% | 14% | 20% | 22%

Through Week 48, 84% and 73% of subjects in the emtricitabine + VIREAD group and the zidovudine/lamivudine group, respectively, achieved and maintained HIV-1 RNA <400 copies/mL (71% and 58% through Week 144). The difference in the proportion of subjects who achieved and maintained HIV-1 RNA <400 copies/mL through 48 weeks largely results from the higher number of discontinuations due to adverse events and other reasons in the zidovudine/lamivudine group in this open-label trial. In addition, 80% and 70% of subjects in the emtricitabine + VIREAD group and the zidovudine/lamivudine group, respectively, achieved and maintained HIV-1 RNA <50 copies/mL through Week 48 (64% and 56% through Week 144). The mean increase from baseline in CD4^+ cell count was 190 cells/mm^3 in the EMTRIVA + VIREAD group and 158 cells/mm^3 in the zidovudine/lamivudine group at Week 48 (312 and 271 cells/mm^3 at Week 144).

Through 48 weeks, 7 subjects in the emtricitabine + VIREAD group and 5 subjects in the zidovudine/lamivudine group experienced a new CDC Class C event (10 and 6 subjects through 144 weeks).

Treatment-Experienced Adult Patients

Study 907

Study 907 was a 24-week, double-blind placebo-controlled multicenter trial of VIREAD added to a stable background regimen of antiretroviral agents in 550 treatment-experienced subjects. After 24 weeks of blinded trial treatment, all subjects continuing on trial were offered open-label VIREAD for an additional 24 weeks. Subjects had a mean baseline CD4^+ cell count of 427 cells/mm^3 (range 23–1385), median baseline plasma HIV-1 RNA of 2340 (range 50–75,000) copies/mL, and mean duration of prior HIV-1 treatment was 5.4 years. Mean age of the subjects was 42 years, 85% were male and 69% were Caucasian, 17% Black and 12% Hispanic.

The percent of subjects with HIV-1 RNA <400 copies/mL and outcomes of subjects through 48 weeks are summarized in Table 19.

Table 19 Outcomes of Randomized Treatment (Study 907)
Outcomes | 0–24 weeks |  | 0–48 weeks | 24–48 weeks
Outcomes | VIREAD (N=368) | Placebo (N=182) | VIREAD (N=368) | Placebo Crossover to VIREAD (N=170)
HIV-1 RNA <400 copies/mL [Subjects with HIV-1 RNA <400 copies/mL and no prior study drug discontinuation at Week 24 and 48 respectively.] | 40% | 11% | 28% | 30%
Virologic failure [Subjects with HIV-1 RNA ≥400 copies/mL efficacy failure or missing HIV-1 RNA at Week 24 and 48 respectively.] | 53% | 84% | 61% | 64%
Discontinued due to adverse event | 3% | 3% | 5% | 5%
Discontinued for other reasons [Includes lost to follow-up, subject withdrawal, noncompliance, protocol violation and other reasons.] | 3% | 3% | 5% | 1%

At 24 weeks of therapy, there was a higher proportion of subjects in the VIREAD arm compared to the placebo arm with HIV-1 RNA <50 copies/mL (19% and 1%, respectively). Mean change in absolute CD4^+ cell counts by Week 24 was +11 cells/mm^3 for the VIREAD group and -5 cells/mm^3 for the placebo group. Mean change in absolute CD4^+ cell counts by Week 48 was +4 cells/mm^3 for the VIREAD group.

Through Week 24, one subject in the VIREAD group and no subjects in the placebo arm experienced a new CDC Class C event.

14.2 Clinical Efficacy in Adults with Chronic Hepatitis B

HBeAg-Negative Chronic Hepatitis B

Study 0102 was a Phase 3, randomized, double-blind, active-controlled trial of VIREAD 300 mg compared to HEPSERA 10 mg in 375 HBeAg- (anti-HBe+) subjects with compensated liver function, the majority of whom were nucleoside-naïve. The mean age of subjects was 44 years, 77% were male, 25% were Asian, 65% were Caucasian, 17% had previously received alpha-interferon therapy and 18% were nucleoside-experienced (16% had prior lamivudine experience). At baseline, subjects had a mean Knodell necroinflammatory score of 7.8; mean plasma HBV DNA was 6.9 log10 copies/mL; and mean serum ALT was 140 U/L.

HBeAg-Positive Chronic Hepatitis B

Study 0103 was a Phase 3, randomized, double-blind, active-controlled trial of VIREAD 300 mg compared to HEPSERA 10 mg in 266 HBeAg+ nucleoside-naïve subjects with compensated liver function. The mean age of subjects was 34 years, 69% were male, 36% were Asian, 52% were Caucasian, 16% had previously received alpha-interferon therapy, and <5% were nucleoside experienced. At baseline, subjects had a mean Knodell necroinflammatory score of 8.4; mean plasma HBV DNA was 8.7 log10 copies /mL; and mean serum ALT was 147 U/L.

The primary data analysis was conducted after all subjects reached 48 weeks of treatment and results are summarized below.

The primary efficacy endpoint in both trials was complete response to treatment defined as HBV DNA <400 copies/mL (69 IU/mL) and Knodell necroinflammatory score improvement of at least 2 points, without worsening in Knodell fibrosis at Week 48 (Table 20).

Table 20 Histological, Virological, Biochemical, and Serological Response at Week 48
 | 0102 (HBeAg-) |  | 0103 (HBeAg+)
 | VIREAD (N=250) | HEPSERA (N=125) | VIREAD (N=176) | HEPSERA (N=90)
Complete Response | 71% | 49% | 67% | 12%
Histology
Histological Response [Knodell necroinflammatory score improvement of at least 2 points without worsening in Knodell fibrosis.] | 72% | 69% | 74% | 68%
HBV DNA <400 copies/mL (<69 IU/mL) | 93% | 63% | 76% | 13%
ALT Normalized ALT [The population used for analysis of ALT normalization included only subjects with ALT above ULN at baseline.] | 76% | 77% | 68% | 54%
Serology HBeAg Loss/Seroconversion | NA [NA = Not Applicable] | NA | 20%/19% | 16%/16%
HBsAg Loss/Seroconversion | 0/0 | 0/0 | 3%/1% | 0/0

Treatment Beyond 48 Weeks

In Studies 0102 (HBeAg-negative) and 0103 (HBeAg-positive), subjects who completed double-blind treatment (389 and 196 subjects who were originally randomized to VIREAD and HEPSERA, respectively) were eligible to roll over to open-label VIREAD with no interruption in treatment.

In Study 0102, 266 of 347 subjects who entered the open-label period (77%) continued in the study through Week 384. Among subjects randomized to VIREAD followed by open-label treatment with VIREAD, 73% had HBV DNA <400 copies/ml (69 IU/ml), and 63% had ALT normalization at Week 384. Among subjects randomized to HEPSERA followed by open-label treatment with VIREAD, 80% had HBV DNA <400 copies/mL (69 IU/mL) and 70% had ALT normalization through Week 384. At Week 384, both HBsAg loss and seroconversion were approximately 1% in both treatment groups.

In Study 0103, 146 of 238 subjects who entered the open-label period (61%) continued in the study through Week 384. Among subjects randomized to VIREAD, 49% had HBV DNA <400 copies/mL (69 IU/mL), 42% had ALT normalization, and 20% had HBeAg loss (13% seroconversion to anti-HBe antibody) through Week 384. Among subjects randomized to HEPSERA followed by open-label treatment with VIREAD, 56% had HBV DNA <400 copies/mL (69 IU/mL), 50% had ALT normalization, and 28% had HBeAg loss (19% seroconversion to anti-HBe antibody) through Week 384. At Week 384, HBsAg loss and seroconversion were 11% and 8% respectively, in subjects initially randomized to VIREAD and 12% and 10%, respectively, in subjects initially randomized to HEPSERA.

Of the originally randomized and treated 641 subjects in the two studies, liver biopsy data from 328 subjects who received continuing open-label treatment with VIREAD monotherapy were available for analysis at baseline, Week 48 and Week 240. There were no apparent differences between the subset of subjects who had liver biopsy data at Week 240 and those subjects remaining on open-label VIREAD without biopsy data that would be expected to affect histological outcomes at Week 240. Among the 328 subjects evaluated, the observed histological response rates were 80% and 88% at Week 48 and Week 240, respectively. In the subjects without cirrhosis at baseline (Ishak fibrosis score 0-4), 92% (216/235) and 95% (223/235) had either improvement or no change in Ishak fibrosis score at Week 48 and Week 240, respectively. In subjects with cirrhosis at baseline (Ishak fibrosis score 5-6), 97% (90/93) and 99% (92/93) had either improvement or no change in Ishak fibrosis score at Week 48 and Week 240, respectively. Twenty-nine percent (27/93) and 72% (67/93) of subjects with cirrhosis at baseline experienced regression of cirrhosis by Week 48 and Week 240, respectively, with a reduction in Ishak fibrosis score of at least 2 points. No definitive conclusions can be established about the remaining study population who were not part of this subset analysis.

Patients with Lamivudine-Resistant Chronic Hepatitis B

Study 121 was a randomized, double-blind, active-controlled trial evaluating the safety and efficacy of VIREAD compared to an unapproved antiviral regimen in subjects with chronic hepatitis B, persistent viremia (HBV DNA ≥ 1,000 IU/mL), and genotypic evidence of lamivudine resistance (rtM204I/V +/- rtL180M). One hundred forty-one adult subjects were randomized to the VIREAD treatment arm. The mean age of subjects randomized to VIREAD was 47 years (range 18–73), 74% were male, 59% were Caucasian, and 37% were Asian. At baseline, 54% of subjects were HBeAg-negative, 46% were HBeAg-positive, and 56% had abnormal ALT. Subjects had a mean HBV DNA of 6.4 log10 copies/mL and mean serum ALT of 71 U/L at baseline.

After 96 weeks of treatment, 126 of 141 subjects (89%) randomized to VIREAD had HBV DNA < 400 copies/mL (69 IU/mL), and 49 of 79 subjects (62%) with abnormal ALT at baseline had ALT normalization. Among the HBeAg-positive subjects randomized to VIREAD, 10 of 65 subjects (15%) experienced HBeAg loss, and 7 of 65 subjects (11%) experienced anti-HBe seroconversion through Week 96. The proportion of subjects with HBV DNA concentrations below 400 copies/mL (69 IU/mL) at Week 96 was similar between the VIREAD monotherapy and the comparator arms.

Across the combined chronic hepatitis B treatment trials, the number of subjects with adefovir-resistance associated substitutions at baseline was too small to establish efficacy in this subgroup.

Patients with Chronic Hepatitis B and Decompensated Liver Disease

VIREAD was studied in a small randomized, double-blind, active-controlled trial evaluating the safety of VIREAD compared to other antiviral drugs in subjects with chronic hepatitis B and decompensated liver disease through 48 weeks (Study 0108).

Forty-five adult subjects (37 males and 8 females) were randomized to the VIREAD treatment arm. At baseline, 69% subjects were HBeAg-negative, and 31% were HBeAg-positive. Subjects had a mean Child-Pugh score of 7, a mean MELD score of 12, mean HBV DNA of 5.8 log10 copies/mL and mean serum ALT of 61 U/L at baseline. Trial endpoints were discontinuation due to an adverse event and confirmed increase in serum creatinine ≥ 0.5 mg/dL or confirmed serum phosphorus of < 2 mg/dL [See Adverse Reactions (6.1)].

At 48 weeks, 31/44 (70%) and 12/26 (46%) Viread-treated subjects achieved an HBV DNA < 400 copies/mL (69 IU/mL), and normalized ALT, respectively. The trial was not designed to evaluate treatment impact on clinical endpoints such as progression of liver disease, need for liver transplantation, or death.

16 HOW SUPPLIED/STORAGE AND HANDLING

VIREAD tablets, 300 mg, are almond-shaped, light blue, film-coated tablets containing 300 mg of tenofovir disoproxil fumarate, which is equivalent to 245 mg of tenofovir disoproxil, are debossed with "GILEAD" and "4331" on one side and with "300" on the other side. Each bottle contains 30 tablets, a desiccant (silica gel canister or sachet), and closed with a child-resistant closure. (NDC 61958-0401-1)

NDC 69189-0401-1 single dose pack with 1 tablet as repackaged by Avera McKennan Hospital

Oral Powder

VIREAD oral powder consists of white, coated granules containing 40 mg of tenofovir disoproxil fumarate, which is equivalent to 33 mg of tenofovir disoproxil, per gram of powder and is available in multi-use bottles containing 60 grams of oral powder, closed with a child-resistant closure, and co-packaged with a dosing scoop. (NDC 61958-0403-1)

STORAGE AND HANDLING

Store VIREAD tablets and oral powder at 25 °C (77 °F), excursions permitted to 15–30 °C (59–86 °F) (see USP Controlled Room Temperature).

Keep the bottle tightly closed. Dispense only in original container. Do not use if seal over bottle opening is broken or missing.

17 PATIENT COUNSELING INFORMATION

Advise the patient to read the FDA-approved patient labeling (Patient Information and Instructions for Use).

- VIREAD is not a cure for HIV-1 infection and patients may continue to experience illnesses associated with HIV-1 infection, including opportunistic infections. Patients should remain under the care of a physician when using VIREAD.
- Patients should avoid doing things that can spread HIV or HBV to others.
  - Do not share needles or other injection equipment.
  - Do not share personal items that can have blood or body fluids on them, like toothbrushes and razor blades.
  - Do not have any kind of sex without protection. Always practice safer sex by using a latex or polyurethane condom to lower the chance of sexual contact with semen, vaginal secretions, or blood.
  - Do not breastfeed. Tenofovir is excreted in breast milk and it is not known whether it can harm the baby. Mothers with HIV-1 should not breastfeed because HIV-1 can be passed to the baby in the breast milk.
- The long-term effects of VIREAD are unknown.
- VIREAD tablets and oral powder are for oral ingestion only.
- VIREAD should not be discontinued without first informing their physician.
- If you have HIV-1 infection, with or without HBV coinfection, it is important to take VIREAD with combination therapy.
- It is important to take VIREAD on a regular dosing schedule and to avoid missing doses.
- Lactic acidosis and severe hepatomegaly with steatosis, including fatal cases, have been reported. Treatment with VIREAD should be suspended in any patient who develops clinical symptoms suggestive of lactic acidosis or pronounced hepatotoxicity (including nausea, vomiting, unusual or unexpected stomach discomfort, and weakness) [See Warnings and Precautions (5.1)].
- Severe acute exacerbations of hepatitis have been reported in patients who are infected with HBV or coinfected with HBV and HIV-1 and have discontinued VIREAD [See Warnings and Precautions (5.2)].
- Renal impairment, including cases of acute renal failure and Fanconi syndrome, has been reported. VIREAD should be avoided with concurrent or recent use of a nephrotoxic agent (e.g., high-dose or multiple NSAIDs) [See Warnings and Precautions (5.3)]. Dosing interval of VIREAD may need adjustment in patients with renal impairment [See Dosage and Administration (2.3)].
- VIREAD should not be coadministered with the fixed-dose combination products ATRIPLA, COMPLERA, STRIBILD, and TRUVADA since it is a component of these products [See Warnings and Precautions (5.4)].
- VIREAD should not be administered in combination with HEPSERA [See Warnings and Precautions (5.4)].
- Patients with HIV-1 should be tested for Hepatitis B virus (HBV) before initiating antiretroviral therapy [See Warnings and Precautions (5.5)].
- In patients with chronic hepatitis B, it is important to obtain HIV antibody testing prior to initiating VIREAD [See Warnings and Precautions (5.5)].
- Decreases in bone mineral density have been observed with the use of VIREAD. Bone mineral density monitoring should be considered in patients who have a history of pathologic bone fracture or at risk for osteopenia [See Warnings and Precautions (5.6)].
- In the treatment of chronic hepatitis B, the optimal duration of treatment is unknown. The relationship between response and long-term prevention of outcomes such as hepatocellular carcinoma is not known.

PATIENT INFORMATION
VIREAD® (VEER-ee-ad)
(tenofovir disoproxil fumarate)
tablets and oral powder

Read this Patient Information before you start taking VIREAD and each time you get a refill. There may be new information. This information does not take the place of talking with your healthcare provider about your medical condition or your treatment.

What is the most important information I should know about VIREAD?

VIREAD can cause serious side effects, including:

1. Build-up of an acid in your blood (lactic acidosis). Lactic acidosis can happen in some people who take VIREAD. Lactic acidosis is a serious medical emergency that can lead to death.
  Lactic acidosis can be hard to identify early, because the symptoms could seem like symptoms of other health problems. Call your healthcare provider right away if you get the following symptoms which could be signs of lactic acidosis:
  - feeling very weak or tired
  - have unusual (not normal) muscle pain
  - have trouble breathing
  - have stomach pain with
    - nausea (feel sick to your stomach)
    - vomiting
  - feel cold, especially in your arms and legs
  - feel dizzy or lightheaded
  - have a fast or irregular heartbeat
2. Severe liver problems. Severe liver problems can happen in people who take VIREAD or similar medicines. In some cases these liver problems can lead to death. Your liver may become large (hepatomegaly) and you may develop fat in your liver (steatosis) when you take VIREAD.
  Call your healthcare provider right away if you have any of the following symptoms of liver problems:
  - your skin or the white part of your eyes turns yellow (jaundice).
  - dark "tea-colored" urine
  - light-colored bowel movements (stools)
  - loss of appetite for several days or longer
  - nausea
  - stomach pain

You may be more likely to get lactic acidosis or severe liver problems if you are female, very overweight (obese), or have been taking VIREAD for a long time.

3. Worsening of your Hepatitis B infection. Your hepatitis B Virus (HBV) infection may become worse (flare-up) if you take VIREAD and then stop it. A "flare-up" is when your HBV infection suddenly returns in a worse way than before.
  - Do not let your VIREAD run out. Refill your prescription or talk to your healthcare provider before your VIREAD is all gone.
  - Do not stop taking VIREAD without first talking to your healthcare provider.
  - If you stop taking VIREAD, your healthcare provider will need to check your health often and do blood tests regularly to check your HBV infection. Tell your healthcare provider about any new or unusual symptoms you may have after you stop taking VIREAD.
4. Talk to your doctor about taking an HIV test before starting treatment with VIREAD for chronic hepatitis B. You should also get a test for HBV if you are taking VIREAD for treatment of HIV.

What is VIREAD?

VIREAD is a prescription medicine used:

1. with other antiviral medicines to treat Human Immunodeficiency Virus-1 (HIV-1) in people 2 years of age and older. HIV is the virus that causes AIDS (Acquired Immune Deficiency Syndrome).
  - When used with other HIV medicines, VIREAD may reduce the amount of HIV in your blood (called "viral load"). VIREAD may also help to increase the number of CD4 (T) cells in your blood which help fight off other infections. Reducing the amount of HIV and increasing the CD4 (T) cell count may improve your immune system. This may reduce your risk of death or infections that can happen when your immune system is weak (opportunistic infections).
  - VIREAD does not cure HIV infection or AIDS. People taking VIREAD may still develop infections or other conditions associated with HIV infection.
  - You must stay on continuous HIV therapy to control infection and decrease HIV-related illnesses.
  - It is very important that you stay under the care of your healthcare provider.
  - It is not known if VIREAD is safe and effective for the treatment of HIV-1 infection in children under the age of 2 years.
2. to treat chronic (long-lasting) hepatitis B virus (HBV) in people 12 years of age and older.
  - VIREAD will not cure HBV.
  - VIREAD may lower the amount of HBV in your body.
  - VIREAD may improve the condition of your liver.
  - The long-term effects of taking VIREAD for treatment of chronic hepatitis B infection are not known.
  - It is not known if VIREAD is safe and effective for treatment of chronic hepatitis B in children under the age of 12 years.

What should I tell my healthcare provider before taking VIREAD?

Before you take VIREAD, tell your healthcare provider if you:

- have liver problems, including hepatitis B (HBV) infection.
- have kidney problems.
- have bone problems.
- have any other medical conditions, including HIV infection.
- are pregnant or plan to become pregnant. It is not known if VIREAD will harm your unborn baby.
  Pregnancy Registry. There is a pregnancy registry for women who take antiviral medicines during pregnancy. Its purpose is to collect information about the health of you and your baby. Talk to your healthcare provider about how you can take part in this registry.
- are breastfeeding or plan to breastfeed. Do not breastfeed if you are taking VIREAD. Tenofovir passes into your breast milk. You should not breastfeed because of the risk of passing HIV to your baby. Talk to your healthcare provider about the best way to feed your baby.

Tell your healthcare provider about all the medicines you take, including prescription and non-prescription medicines, vitamins and herbal supplements. VIREAD may affect the way other medicines work, and other medicines may affect how VIREAD works.

Do not take VIREAD if you also take:

- other medicines that contain tenofovir (ATRIPLA®, COMPLERA®, STRIBILD®, TRUVADA®)
- adefovir (HEPSERA®)

Especially tell your healthcare provider if you take the following medications.

- didanosine (Videx, Videx EC)
- atazanavir (Reyataz)
- darunavir (Prezista)
- lopinavir with ritonavir (Kaletra)

Know the medicines you take. Keep a list of them to show your healthcare provider or pharmacist when you get a new medicine.

How should I take VIREAD?

- See "What is the most important information I should know about VIREAD?"
- Take VIREAD exactly as your healthcare provider tells you to take it.
- Take VIREAD at the same time every day.
- For adults and children 12 years of age and older, the usual dose of VIREAD is one 300 mg tablet each day.
- If you are an adult with kidney problems, your healthcare provider may tell you to take VIREAD less often.
- Adults and children 12 years of age and older who are unable to swallow VIREAD tablets whole may take 7½ scoops of VIREAD oral powder.
- For children 2 to 12 years of age, your healthcare provider will prescribe the right dose of VIREAD oral powder or tablets based on your child's body weight.
- Tell your healthcare provider if your child has problems with swallowing tablets.
- See the "Instructions for Use" section at the end of this Patient Information leaflet for information about the right way to measure and take VIREAD oral powder.
- Take VIREAD tablets by mouth, with or without food.
- Do not miss a dose of VIREAD. If you miss a dose of VIREAD, take the missed dose as soon as you remember. If it is almost time for your next dose of VIREAD, do not take the missed dose. Take the next dose of VIREAD at your regular time.
- If you take too much VIREAD, call your local poison control center or go right away to the nearest hospital emergency room.

What are the possible side effects of VIREAD?

VIREAD may cause serious side effects, including:

- See "What is the most important information I should know about VIREAD?"
- New or worse kidney problems, including kidney failure, can happen in some people who take VIREAD. Your healthcare provider should do blood tests to check your kidneys before you start treatment with VIREAD. If you have had kidney problems in the past or need to take another medicine that can cause kidney problems, your healthcare provider may need to do blood tests to check your kidneys during your treatment with VIREAD.
- Bone problems can happen in some people who take VIREAD. Bone problems include bone pain, softening or thinning (which may lead to fractures). Your healthcare provider may need to do additional tests to check your bones.
- Changes in body fat can happen in some people who take antiviral medicines. These changes may include increased amount of fat in the upper back and neck ("buffalo hump"), breast, and around the main part of your body (trunk). Loss of fat from the legs, arms, and face may also happen. The cause and long-term health effects of these conditions are not known.
- Changes in your immune system (Immune Reconstitution Syndrome) can happen when you start taking HIV medicines. Your immune system may get stronger and begin to fight infections that have been hidden in your body for a long time. Tell your healthcare provider if you start having new symptoms after starting your HIV medicine.

The most common side effects in all people who take VIREAD are:

- nausea
- rash
- diarrhea
- headache

- pain
- depression
- weakness

In some people with advanced HBV-infection, other common side effects may include:

- sleeping problems
- itching
- vomiting
- dizziness
- fever

Tell your healthcare provider if you have any side effect that bothers you or that does not go away.

These are not all the possible side effects of VIREAD. For more information, ask your healthcare provider or pharmacist.

Call your doctor for medical advice about side effects. You may report side effects to FDA at 1-800-FDA-1088.

How should I store VIREAD?

- Store VIREAD tablets or oral powder at room temperature between 68 °F to 77 °F (20 °C to 25 °C).
- Keep VIREAD in the original container.
- Do not use VIREAD if the seal over the bottle opening is broken or missing.
- Keep the bottle tightly closed.

Keep VIREAD and all medicines out of the reach of children.

General information about VIREAD:

Medicines are sometimes prescribed for purposes other than those listed in a Patient Information leaflet. Do not use VIREAD for a condition for which it was not prescribed. Do not give VIREAD to other people, even if they have the same condition you have. It may harm them.

Avoid doing things that can spread HIV-1 or HBV infection to others.

- Do not share or re-use needles or other injection equipment.
- Do not share personal items that can have blood or body fluids on them, like toothbrushes and razor blades.
- Do not have any kind of sex without protection. Always practice safe sex by using a latex or polyurethane condom to lower the chance of sexual contact with semen, vaginal secretions, or blood.

A vaccine is available to protect people at risk for becoming infected with HBV. You can ask your healthcare provider for information about this vaccine.

This leaflet summarizes the most important information about VIREAD. If you would like more information, talk with your healthcare provider. You can ask your pharmacist or healthcare provider for information about VIREAD that is written for health professionals.

For more information, go to www.viread.com or call Gilead Sciences, Inc. at 1-800-GILEAD-5 (1-800-445-3235).

What are the ingredients in VIREAD?

Active Ingredient: tenofovir disoproxil fumarate

Inactive Ingredients:

VIREAD tablets: croscarmellose sodium, lactose monohydrate, magnesium stearate, microcrystalline cellulose, and pregelatinized starch.

VIREAD Oral Powder: mannitol, hydroxypropyl cellulose, ethylcellulose, and silicon dioxide.

Tablet Coating:

VIREAD tablets 300 mg: Opadry II Y-30-10671-A, which contains FD&C blue #2 aluminum lake, hypromellose 2910, lactose monohydrate, titanium dioxide, and triacetin.

VIREAD tablets 150, 200 and 250 mg: Opadry II 32K-18425, which contains hypromellose 2910, lactose monohydrate, titanium dioxide, and triacetin.

Manufactured for and distributed by:
Gilead Sciences, Inc.
Foster City, CA 94404

Revised: May 2015

COMPLERA, EMTRIVA, GSI, HEPSERA, STRIBILD, TRUVADA, and VIREAD are trademarks or registered trademarks of Gilead Sciences, Inc., or its related companies. ATRIPLA is a registered trademark of Bristol-Myers Squibb & Gilead Sciences, LLC. All other trademarks herein are the property of their respective owners.

21-356-GS-036